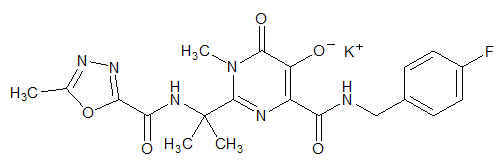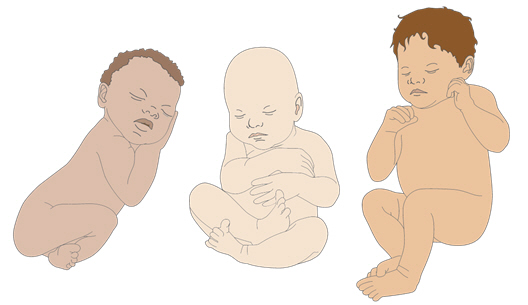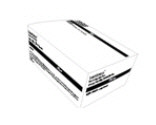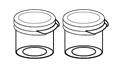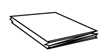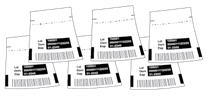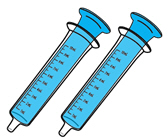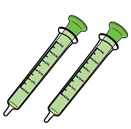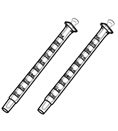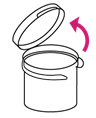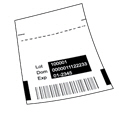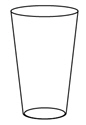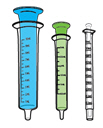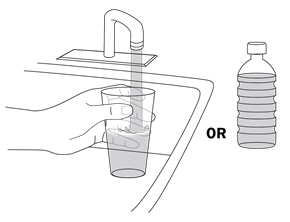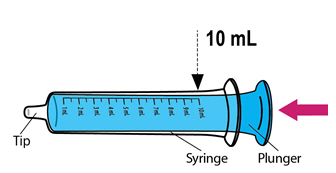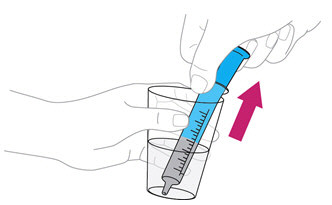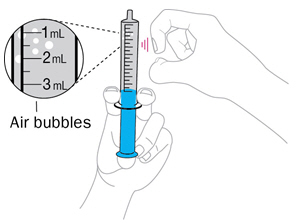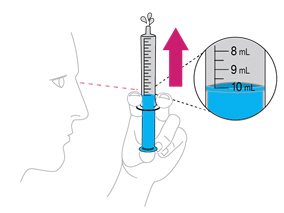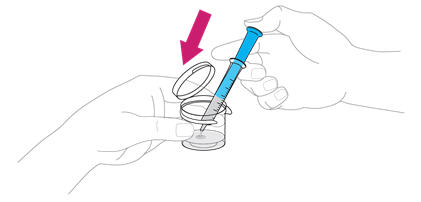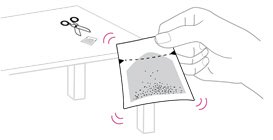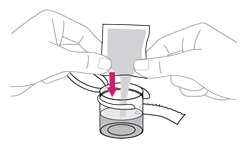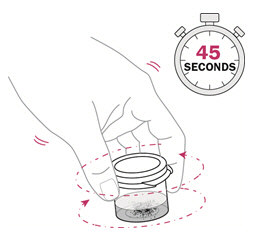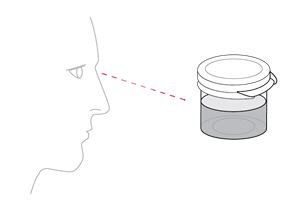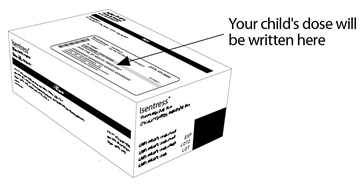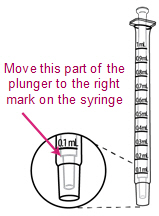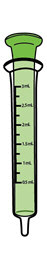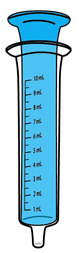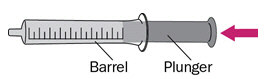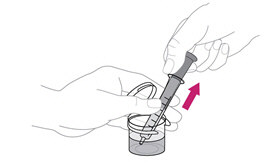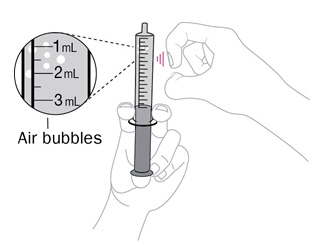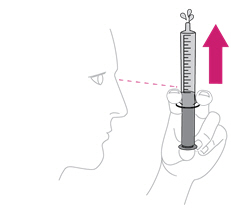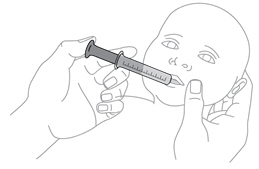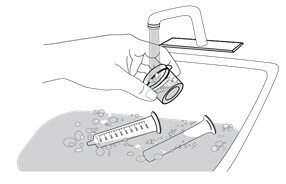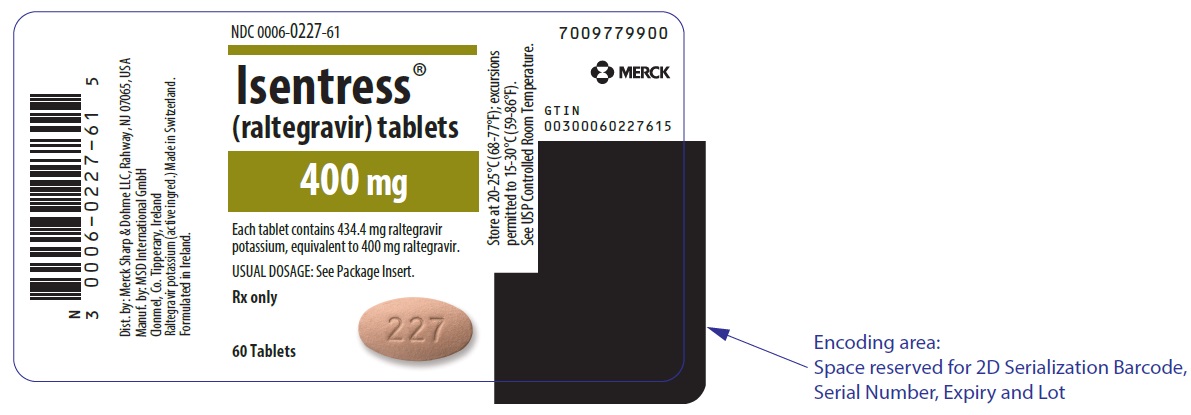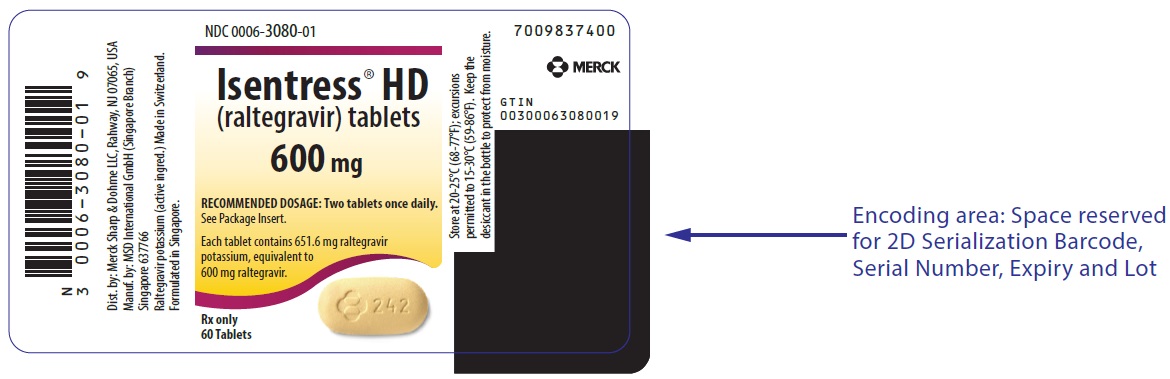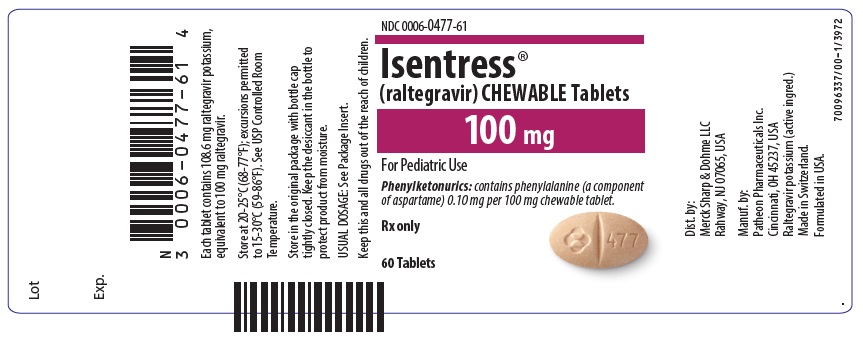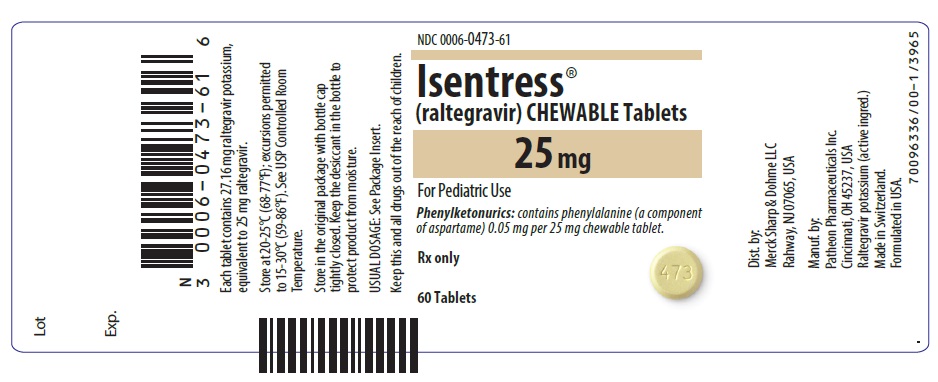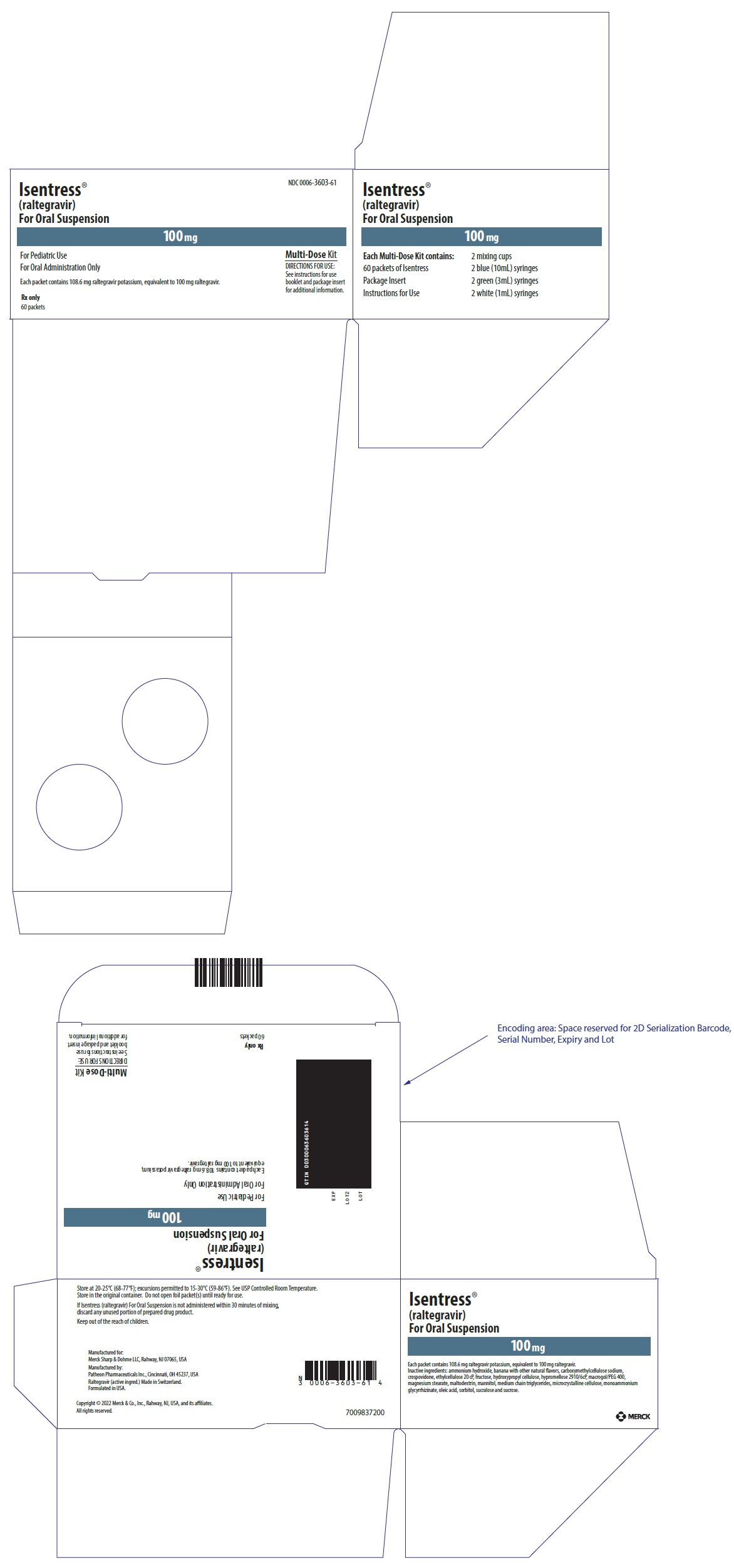 DRUG LABEL: ISENTRESS
NDC: 0006-0227 | Form: TABLET, FILM COATED
Manufacturer: Merck Sharp & Dohme LLC
Category: prescription | Type: HUMAN PRESCRIPTION DRUG LABEL
Date: 20241018

ACTIVE INGREDIENTS: RALTEGRAVIR POTASSIUM 400 mg/1 1
INACTIVE INGREDIENTS: FERROSOFERRIC OXIDE; BUTYLATED HYDROXYTOLUENE; ANHYDROUS DIBASIC CALCIUM PHOSPHATE; HYPROMELLOSE, UNSPECIFIED; LACTOSE MONOHYDRATE; MAGNESIUM STEARATE; MICROCRYSTALLINE CELLULOSE; POLOXAMER 407; POLYETHYLENE GLYCOL 3350; POLYVINYL ALCOHOL, UNSPECIFIED; FERRIC OXIDE RED; SODIUM STEARYL FUMARATE; TALC; TITANIUM DIOXIDE

HIGHLIGHTS OF PRESCRIBING INFORMATION

These highlights do not include all the information needed to use ISENTRESS safely and effectively. See full prescribing information for ISENTRESS.
ISENTRESS® (raltegravir) film-coated tablets, for oral use
ISENTRESS® HD (raltegravir) film-coated tablets, for oral use
ISENTRESS® (raltegravir) chewable tablets, for oral use
ISENTRESS® (raltegravir) for oral suspension
Initial U.S. Approval: 2007

1 INDICATIONS AND USAGE

Adult Patients:

ISENTRESS and ISENTRESS HD are human immunodeficiency virus integrase strand transfer inhibitors (HIV-1 INSTI) indicated in combination with other antiretroviral agents for the treatment of HIV-1 infection in adult patients (1).

Pediatric Patients:

ISENTRESS is indicated in combination with other antiretroviral agents for the treatment of HIV-1 infection in pediatric patients weighing at least 2 kg (1).

ISENTRESS HD is indicated in combination with other antiretroviral agents for the treatment of HIV-1 infection in pediatric patients weighing at least 40 kg (1).

2 DOSAGE AND ADMINISTRATION

ISENTRESS and ISENTRESS HD can be administered with or without food (2.1).

Do not substitute ISENTRESS chewable tablets or ISENTRESS for oral suspension for the ISENTRESS 400 mg or 600 mg film-coated tablet.

See specific dosing guidance for chewable tablets and the formulation for oral suspension (2.1).

Adults

- Treatment-naïve patients or patients who are virologically suppressed on an initial regimen of ISENTRESS 400 mg twice daily:
  - 1200 mg (2 × 600 mg) film-coated tablet orally, once daily or
  - 400 mg film-coated tablet orally, twice daily (2.2).
- Treatment-experienced patients:
  - 400 mg film-coated tablet orally, twice daily (2.2).
- During coadministration with rifampin in adults, 800 mg (2 × 400 mg) twice daily (2.2).

Pediatrics

- If weighing at least 40 kg, and either
  - treatment-naïve patients or
  - patients who are virologically suppressed on an initial regimen of ISENTRESS 400 mg twice daily:
    - 1200 mg (2 × 600 mg) film-coated tablet orally, once daily or
    - 400 mg film-coated tablet orally, twice daily or
    - 300 mg (3 × 100 mg) chewable tablets, twice daily (2.3).
- If weighing at least 25 kg: One 400 mg film-coated tablet orally, twice daily. If unable to swallow a tablet, consider the chewable tablet, as specified in Table 2 (2.3).
- If weighing at least 3 kg to less than 25 kg: Weight-based dosing using the chewable tablet or oral suspension, as specified in Table 4 (2.3).
- For neonates (birth to 4 weeks [28 days] of age): Weight-based dosing of the oral suspension as specified in Table 5 (2.3).

3 DOSAGE FORMS AND STRENGTHS

- Film-Coated Tablets: 400 mg (3).
- Film-Coated Tablets: 600 mg (3).
- Chewable Tablets: 100 mg scored and 25 mg (3).
- For Oral Suspension: Single-use packet of 100 mg (3).

4 CONTRAINDICATIONS

None (4).

5 WARNINGS AND PRECAUTIONS

- Severe, potentially life-threatening and fatal skin reactions have been reported. This includes cases of Stevens-Johnson syndrome, hypersensitivity reaction and toxic epidermal necrolysis. Immediately discontinue treatment with ISENTRESS or ISENTRESS HD and other suspect agents if severe hypersensitivity, severe rash, or rash with systemic symptoms or liver aminotransferase elevations develops and monitor clinical status, including liver aminotransferases closely (5.1).
- Monitor for Immune Reconstitution Syndrome (5.2).
- Inform patients with phenylketonuria that the 100 mg and 25 mg chewable tablets contain phenylalanine (5.3).

6 ADVERSE REACTIONS

- The most common adverse reactions of moderate to severe intensity (≥2%) are insomnia, headache, dizziness, nausea and fatigue (6.1).
- Creatine kinase elevations were observed in subjects who received ISENTRESS or ISENTRESS HD. Myopathy and rhabdomyolysis have been reported. Use with caution in patients at increased risk of myopathy or rhabdomyolysis, such as patients receiving concomitant medications known to cause these conditions and patients with a history of rhabdomyolysis, myopathy or increased serum creatine kinase (6.2).

To report SUSPECTED ADVERSE REACTIONS, contact Merck Sharp & Dohme LLC at 1-877-888-4231 or FDA at 1-800-FDA-1088 or www.fda.gov/medwatch.

7 DRUG INTERACTIONS

- Coadministration of ISENTRESS or ISENTRESS HD and other drugs may alter the plasma concentration of raltegravir. The potential for drug-drug interactions must be considered prior to and during therapy (7).
- Coadministration of ISENTRESS or ISENTRESS HD with drugs that are strong inducers of UGT1A1, such as rifampin, may result in reduced plasma concentrations of raltegravir (2.1, 7.1).

8 USE IN SPECIFIC POPULATIONS

Lactation: Women infected with HIV should be instructed not to breastfeed due to the potential for HIV transmission (8.2).

FULL PRESCRIBING INFORMATION

1 INDICATIONS AND USAGE

Adult Patients:

ISENTRESS® and ISENTRESS® HD are indicated in combination with other antiretroviral agents for the treatment of human immunodeficiency virus (HIV-1) infection in adult patients.

Pediatric Patients:

ISENTRESS is indicated in combination with other antiretroviral agents for the treatment of HIV-1 infection in pediatric patients weighing at least 2 kg.

ISENTRESS HD is indicated in combination with other antiretroviral agents for the treatment of HIV-1 infection in pediatric patients weighing at least 40 kg.

2 DOSAGE AND ADMINISTRATION

2.1 General Dosing Recommendations

- Because the formulations have different pharmacokinetic profiles, do not substitute ISENTRESS chewable tablets or ISENTRESS for oral suspension for the ISENTRESS 400 mg film-coated tablet or the ISENTRESS HD 600 mg film-coated tablet. See specific dosing guidance for chewable tablets and the formulation for oral suspension.
- Because the extent to which ISENTRESS may be dialyzable is unknown, dosing before a dialysis session should be avoided [see Clinical Pharmacology (12.3)].
- ISENTRESS film-coated tablets must be swallowed whole.
- ISENTRESS chewable tablets may be chewed or swallowed whole. Maximum daily dose is 300 mg taken by mouth twice daily.
- For children who have difficulty chewing the 25 mg chewable tablet, the tablet may be crushed.
  - Preparation of the crushed 25 mg chewable tablet:
    - Place the tablet(s) in a small, clean cup. For each tablet, add a teaspoonful (~5 mL) of liquid (for example, water, juice, or breast milk).
    - Within 2 minutes, the tablet(s) will absorb the liquid and fall apart.
    - Using a spoon, crush any remaining pieces of the tablet(s). Immediately administer the entire dose orally.
    - If any portion of the dose is left in the cup, add another teaspoonful (~5 mL) of liquid, swirl and administer immediately.
- ISENTRESS for oral suspension:
  - See Instructions for Use for details on preparation and administration of ISENTRESS for oral suspension.
  - Using the provided mixing cup, combine 10 mL of water and the entire contents of one packet of ISENTRESS for oral suspension and mix. Each single-use packet for oral suspension contains 100 mg of raltegravir which is suspended in 10 mL of water giving a final concentration of 10 mg per mL. Maximum daily dose is 100 mg taken by mouth twice daily.
  - Gently swirl the mixing cup for 45 seconds in a circular motion to mix the powder into a uniform suspension. Do not shake.
  - Once mixed, measure the prescribed dose volume of suspension with a syringe and administer the dose orally. The dose should be administered orally within 30 minutes of mixing.
  - Discard any remaining suspension into the trash.

2.2 Adults

The recommended adult dosage of ISENTRESS film-coated tablets is displayed in Table 1. ISENTRESS and ISENTRESS HD should be taken by mouth and may be taken with or without food [see Clinical Pharmacology (12.3)].

Table 1: Dosing Recommendations for ISENTRESS and ISENTRESS HD in Adult Patients
Population | Recommended Dose
Treatment-naïve patients or patients who are virologically suppressed on an initial regimen of ISENTRESS 400 mg twice daily | 1200 mg (2 × 600 mg) once daily or 400 mg twice daily
Treatment-experienced | 400 mg twice daily
Treatment-naïve or treatment-experienced when coadministered with rifampin [see Drug Interactions (7.1)] | 800 mg (2 × 400 mg) twice daily

2.3 Pediatrics

The recommended pediatric dosage of ISENTRESS is displayed in Table 2. ISENTRESS film-coated tablets, chewable tablets and for oral suspension should be taken by mouth and may be taken with or without food [see Clinical Pharmacology (12.3)].

Table 2: Dosing Recommendations for ISENTRESS and ISENTRESS HD in Pediatric Patients
 | Recommended Pediatric Dosage and Formulation
Population/Weight | Film-Coated Tablets 400 mg | Film-Coated Tablets 600 mg | Chewable Tablets 100 mg and 25 mg | For Oral Suspension 100 mg
If at least 40 kg and either:; - treatment-naïve or - virologically suppressed on an initial regimen of ISENTRESS 400 mg twice daily | 400 mg twice daily | 1200 mg (2 × 600 mg) once daily | 300 mg twice daily (see Table 3) | NA
If at least 25 kg | 400 mg twice daily [If able to swallow a tablet] | NA | Weight-based dosing twice daily (see Table 3) | NA
If at least 4 weeks of age and weighing 3 kg to less than 25 kg | NA | NA | Weight-based dosing twice daily (see Table 4) | Weight-based dosing twice daily up to 20 kg (see Table 4)
From birth to 4 weeks (28 days) weighing at least 2 kg | NA | NA | NA | Weight-based dosing once daily or twice daily (see Table 5)

Table 3: Alternative Dosage [The weight-based dosing recommendation for the chewable tablet is based on approximately 6 mg/kg/dose twice daily [see Clinical Pharmacology (12.3)].] with ISENTRESS Chewable Tablets for Pediatric Patients Weighing at Least 25 kg
Body Weight (kg) | Dose | Number of 100 mg Chewable Tablets
25 to less than 28 | 150 mg twice daily | 1.5 × 100 mg [The 100 mg chewable tablet can be divided into equal halves.] twice daily
28 to less than 40 | 200 mg twice daily | 2 × 100 mg twice daily
At least 40 | 300 mg twice daily | 3 × 100 mg twice daily

Table 4: Recommended Dosage [The weight-based dosing recommendation for the chewable tablet and oral suspension is based on approximately 6 mg/kg/dose twice daily [see Clinical Pharmacology (12.3)].] for ISENTRESS For Oral Suspension and Chewable Tablets in Pediatric Patients at Least 4 Weeks of Age and Weighing at Least 3 kg and Less than 25 kg
Body Weight (kg) | Volume (Dose) of Suspension to be Administered | Number of Chewable Tablets [The chewable tablets are available as 25 mg and 100 mg tablets.]
3 to less than 4 | 2.5 mL (25 mg) twice daily | 1 × 25 mg twice daily [May be administered as a crushed tablet(s); see General Dosing Recommendations (2.1) for guidance.]
4 to less than 6 | 3 mL (30 mg) twice daily
6 to less than 8 | 4 mL (40 mg) twice daily | 2 × 25 mg twice daily
8 to less than 10 | 6 mL (60 mg) twice daily
10 to less than 14 | 8 mL (80 mg) twice daily | 3 × 25 mg twice daily
14 to less than 20 | 10 mL (100 mg) twice daily | 1 × 100 mg twice daily
20 to less than 25 | Not applicable | 1.5 × 100 mg [The 100 mg chewable tablet can be divided into equal halves.] twice daily

- For full-term neonates (birth to 4 weeks [28 days] of age): Weight-based dosing of the oral suspension as specified in Table 5.
- No data are available in pre-term neonates. The use of ISENTRESS is not recommended in pre-term neonates.

Table 5: Recommended Dose for ISENTRESS For Oral Suspension in Full-Term Neonates (Birth to 4 Weeks [28 days] of Age)
Body Weight (kg) | Volume (Dose) of Suspension to be Administered
Birth to 1 Week - Once daily dosing [The dosing recommendations are based on approximately 1.5 mg/kg/dose.]
2 to less than 3 | 0.4 mL (4 mg) once daily
3 to less than 4 | 0.5 mL (5 mg) once daily
4 to less than 5 | 0.7 mL (7 mg) once daily
1 to 4 Weeks - Twice daily dosing [The dosing recommendations are based on approximately 3 mg/kg/dose.]
2 to less than 3 | 0.8 mL (8 mg) twice daily
3 to less than 4 | 1 mL (10 mg) twice daily
4 to less than 5 | 1.5 mL (15 mg) twice daily
Note: If the mother has taken ISENTRESS or ISENTRESS HD 2-24 hours before delivery, the neonate's first dose should be given between 24-48 hours after birth.

3 DOSAGE FORMS AND STRENGTHS

- Film-coated Tablets
  - 400 mg pink, oval-shaped, film-coated tablets with "227" on one side (ISENTRESS).
  - 600 mg yellow, oval-shaped, film-coated tablets with corporate logo and "242" on one side and plain on the other side (ISENTRESS HD).
- Chewable Tablets
  - 100 mg pale orange, oval-shaped, orange-banana flavored, chewable tablets scored on both sides and imprinted on one face with the corporate logo and "477" on opposite sides of the score.
  - 25 mg pale yellow, round, orange-banana flavored, chewable tablets with the corporate logo on one side and "473" on the other side.
- For Oral Suspension
  - 100 mg white to off-white, banana flavored, granular powder that may contain yellow or beige to tan particles in a child resistant single-use foil packet.

4 CONTRAINDICATIONS

None

5 WARNINGS AND PRECAUTIONS

5.1 Severe Skin and Hypersensitivity Reactions

Severe, potentially life-threatening, and fatal skin reactions have been reported. These include cases of Stevens-Johnson syndrome and toxic epidermal necrolysis. Hypersensitivity reactions have also been reported and were characterized by rash, constitutional findings, and sometimes, organ dysfunction, including hepatic failure. Discontinue ISENTRESS or ISENTRESS HD and other suspect agents immediately if signs or symptoms of severe skin reactions or hypersensitivity reactions develop (including, but not limited to, severe rash or rash accompanied by fever, general malaise, fatigue, muscle or joint aches, blisters, oral lesions, conjunctivitis, facial edema, hepatitis, eosinophilia, angioedema). Clinical status including liver aminotransferases should be monitored and appropriate therapy initiated. Delay in stopping ISENTRESS or ISENTRESS HD treatment or other suspect agents after the onset of severe rash may result in a life-threatening reaction.

5.2 Immune Reconstitution Syndrome

Immune reconstitution syndrome has been reported in patients treated with combination antiretroviral therapy, including ISENTRESS. During the initial phase of combination antiretroviral treatment, patients whose immune systems respond may develop an inflammatory response to indolent or residual opportunistic infections (such as Mycobacterium avium infection, cytomegalovirus, Pneumocystis jiroveci pneumonia, tuberculosis), which may necessitate further evaluation and treatment.

Autoimmune disorders (such as Graves' disease, polymyositis, and Guillain-Barré syndrome) have also been reported to occur in the setting of immune reconstitution; however, the time to onset is more variable, and can occur many months after initiation of treatment.

5.3 Phenylketonurics

ISENTRESS Chewable Tablets contain phenylalanine, a component of aspartame. Each 25 mg ISENTRESS Chewable Tablet contains approximately 0.05 mg phenylalanine. Each 100 mg ISENTRESS Chewable Tablet contains approximately 0.10 mg phenylalanine. Phenylalanine can be harmful to patients with phenylketonuria.

6 ADVERSE REACTIONS

Because clinical trials are conducted under widely varying conditions, adverse reaction rates observed in the clinical trials of a drug cannot be directly compared to rates in the clinical trials of another drug and may not reflect the rates observed in practice.

6.1 Clinical Trials Experience

Treatment-Naïve Adults

The safety of ISENTRESS was evaluated in HIV-infected treatment-naïve subjects in 2 Phase III studies: STARTMRK evaluated ISENTRESS 400 mg twice daily versus efavirenz, both in combination with emtricitabine (+) tenofovir disoproxil fumarate (TDF), and ONCEMRK evaluated ISENTRESS HD 1200 mg (2 × 600 mg) once daily versus ISENTRESS 400 mg twice daily, both in combination with emtricitabine (+) tenofovir disoproxil fumarate. Safety data from these two studies are presented side-by-side in Tables 6 and 7 to simplify presentation; direct comparisons across trials should not be made due to differing duration of follow-up and study design.

STARTMRK (ISENTRESS 400 mg twice daily)

In STARTMRK, subjects received ISENTRESS 400 mg twice daily (N=281) or efavirenz (EFV) 600 mg at bedtime (N=282) both in combination with emtricitabine (+) tenofovir disoproxil fumarate, (N=282). During double-blind treatment, the total follow-up for subjects receiving ISENTRESS 400 mg twice daily + emtricitabine (+) tenofovir disoproxil fumarate was 1104 patient-years and 1036 patient-years for subjects receiving efavirenz 600 mg at bedtime + emtricitabine (+) tenofovir disoproxil fumarate.

In STARTMRK, the rate of discontinuation of therapy due to adverse events through Week 240 was 5% in subjects receiving ISENTRESS + emtricitabine (+) tenofovir disoproxil fumarate and 10% in subjects receiving efavirenz + emtricitabine (+) tenofovir disoproxil fumarate.

ONCEMRK (ISENTRESS HD 1200 mg [2 × 600 mg] once daily)

In ONCEMRK, subjects received ISENTRESS HD 1200 mg once daily (n=531) or ISENTRESS 400 mg twice daily (n=266) both in combination with emtricitabine (+) tenofovir disoproxil fumarate. During double-blind treatment, the total follow-up for subjects with ISENTRESS HD 1200 mg once daily was 913 patient-years and for ISENTRESS 400 mg twice daily was 450 patient-years.

In ONCEMRK, the rate of discontinuation of therapy due to adverse events through Week 96 was 1% in subjects receiving ISENTRESS HD 1200 mg (2 × 600 mg) once daily and 2% in subjects receiving ISENTRESS 400 mg twice daily.

Clinical adverse reactions of moderate to severe intensity occurring in ≥2% of treatment-naïve subjects treated with ISENTRESS 400 mg twice daily or efavirenz in STARTMRK through Week 240 or ISENTRESS HD 1200 mg once daily or ISENTRESS 400 mg twice daily in ONCEMRK through Week 96 are presented in Table 6.

In STARTMRK, clinical adverse reactions of all intensities (mild, moderate and severe) occurring in ≥2% of subjects on ISENTRESS 400 mg twice daily through Week 240 also include diarrhea, flatulence, asthenia, decreased appetite, abnormal dreams, depression and nightmare. In ONCEMRK, clinical adverse reactions of all intensities (mild, moderate and severe) occurring in ≥2% of subjects on ISENTRESS HD or ISENTRESS 400 mg twice daily through Week 96 also include abdominal pain, diarrhea, vomiting, and decreased appetite.

Table 6: Adverse Reactions [Includes adverse experiences considered by investigators to be at least possibly, probably, or definitely related to the drug.] of Moderate to Severe Intensity [Intensities are defined as follows: Moderate (discomfort enough to cause interference with usual activity); Severe (incapacitating with inability to work or do usual activity).] Occurring in ≥2% of Treatment-Naïve Adult Subjects Receiving ISENTRESS and ISENTRESS HD
System Organ Class, Preferred Term | STARTMRK Week 240 |  | ONCEMRK Week 96
System Organ Class, Preferred Term | ISENTRESS 400 mg Twice Daily (N= 281) | Efavirenz 600 mg At Bedtime (N= 282) | ISENTRESS HD 1200 mg Once Daily (N=531) | ISENTRESS 400 mg Twice Daily (N=266)
Headache | 4% | 5% | 1% | <1%
Insomnia | 4% | 4% | <1% | <1%
Nausea | 3% | 4% | 1% | 0%
Dizziness | 2% | 6% | <1% | 0%
Fatigue | 2% | 3% | 0% | 0%
Note: ISENTRESS BID, ISENTRESS HD and efavirenz were administered with emtricitabine (+) tenofovir disoproxil fumarate
N= total number of subjects per treatment group

Laboratory Abnormalities

The percentages of adult subjects with selected Grade 2 to 4 laboratory abnormalities (that represent a worsening Grade from baseline) who were treated with ISENTRESS 400 mg twice daily or efavirenz in STARTMRK or ISENTRESS HD 1200 mg once daily or ISENTRESS 400 mg twice daily in ONCEMRK are presented in Table 7.

Table 7: Selected Grade 2 to 4 Laboratory Abnormalities Reported in Treatment-Naïve Subjects
 |  | STARTMRK Week 240 |  | ONCEMRK Week 96
Laboratory Parameter Preferred Term (Unit) | Limit | ISENTRESS 400 mg Twice Daily (N = 281) | Efavirenz 600 mg At Bedtime (N = 282) | ISENTRESS HD 1200 mg Once Daily (N=531) | ISENTRESS 400 mg Twice Daily (N=266)
Hematology
Absolute neutrophil count (10^3/µL)
Grade 2 | 0.75 - 0.999 | 3% | 5% | 2% | 1%
Grade 3 | 0.50 - 0.749 | 3% | 1% | 1% | 1%
Grade 4 | <0.50 | 1% | 1% | <1% | 0%
Hemoglobin (gm/dL)
Grade 2 | 7.5 - 8.4 | 1% | 1% | 0% | 0%
Grade 3 | 6.5 - 7.4 | 1% | 1% | 0% | 0%
Grade 4 | <6.5 | <1% | 0% | 0% | 0%
Platelet count (10^3/µL)
Grade 2 | 50 - 99.999 | 1% | 0% | 1% | <1%
Grade 3 | 25 - 49.999 | <1% | <1% | 0% | 0%
Grade 4 | <25 | 0% | 0% | 0% | <1%
Blood chemistry
Fasting (non-random) serum glucose test (mg/dL) [Test not done in ONCEMRK]
Grade 2 | 126 - 250 | 7% | 6% | - | -
Grade 3 | 251 - 500 | 2% | 1% | - | -
Grade 4 | >500 | 0% | 0% | - | -
Total serum bilirubin
Grade 2 | 1.6 - 2.5 × ULN | 5% | <1% | 3% | 2%
Grade 3 | 2.6 - 5.0 × ULN | 1% | 0% | 1% | <1%
Grade 4 | >5.0 × ULN | <1% | 0% | <1% | 0%
Creatinine
Grade 2 | 1.4-1.8 × ULN | 1% | 1% | 0% | <1%
Grade 3 | 1.9-3.4 × ULN | 0% | <1% | 0% | 0%
Grade 4 | ≥3.5 × ULN | 0% | 0% | 0% | 0%
Serum aspartate aminotransferase
Grade 2 | 2.6 - 5.0 × ULN | 8% | 10% | 5% | 3%
Grade 3 | 5.1 - 10.0 × ULN | 5% | 3% | 2% | <1%
Grade 4 | >10.0 × ULN | 1% | <1% | 1% | <1%
Serum alanine aminotransferase
Grade 2 | 2.6 - 5.0 × ULN | 11% | 12% | 4% | 2%
Grade 3 | 5.1 - 10.0 × ULN | 2% | 2% | 1% | <1%
Grade 4 | >10.0 × ULN | 2% | 1% | 1% | <1%
Serum alkaline phosphatase
Grade 2 | 2.6 - 5.0 × ULN | 1% | 3% | 1% | 0%
Grade 3 | 5.1 - 10.0 × ULN | 0% | 1% | <1% | 0%
Grade 4 | >10.0 × ULN | <1% | <1% | 0% | 0%
Lipase [Test not done in STARTMRK]
Grade 2 | 1.6-3.0 x ULN | - | - | 7% | 5%
Grade 3 | 3.1-5.0 × ULN | - | - | 2% | 1%
Grade 4 | >5.0 × ULN | - | - | 2% | 1%
Creatine kinase
Grade 2 | 6.0-9.9 × ULN | - | - | 4% | 5%
Grade 3 | 10.0-19.9 × ULN | - | - | 3% | 3%
Grade 4 | ≥20.0 × ULN | - | - | 3% | 2%
ULN = Upper limit of normal range
Notes: ISENTRESS BID, ISENTRESS HD and Efavirenz were administered with emtricitabine (+) tenofovir disoproxil fumarate

Lipids, Change from Baseline

Changes from baseline in fasting lipids are shown in Table 8.

Table 8: Lipid Values, Mean Change from Baseline, STARTMRK Study
Laboratory Parameter Preferred Term | ISENTRESS 400 mg Twice Daily + Emtricitabine (+) Tenofovir Disoproxil Fumarate N = 207 |  |  | Efavirenz 600 mg At Bedtime + Emtricitabine (+) Tenofovir Disoproxil Fumarate N = 187
 |  |  | Change from Baseline at Week 240 |  |  | Change from Baseline at Week 240
 | Baseline Mean | Week 240 Mean | Mean Change | Baseline Mean | Week 240 Mean | Mean Change
 | (mg/dL) | (mg/dL) | (mg/dL) | (mg/dL) | (mg/dL) | (mg/dL)
LDL-Cholesterol [Fasting (non-random) laboratory tests at Week 240.] | 96 | 106 | 10 | 93 | 118 | 25
HDL-Cholesterol | 38 | 44 | 6 | 38 | 51 | 13
Total Cholesterol | 159 | 175 | 16 | 157 | 201 | 44
Triglyceride | 128 | 130 | 2 | 141 | 178 | 37
Notes:
N = total number of subjects per treatment group with at least one lipid test result available. The analysis is based on all available data.
If subjects initiated or increased serum lipid-reducing agents, the last available lipid values prior to the change in therapy were used in the analysis. If the missing data was due to other reasons, subjects were censored thereafter for the analysis. At baseline, serum lipid-reducing agents were used in 5% of subjects in the group receiving ISENTRESS and 3% in the efavirenz group. Through Week 240, serum lipid-reducing agents were used in 9% of subjects in the group receiving ISENTRESS and 15% in the efavirenz group.

Treatment-Experienced Adults

The safety assessment of ISENTRESS in treatment-experienced subjects is based on the pooled safety data from the randomized, double-blind, placebo-controlled trials, BENCHMRK 1 and BENCHMRK 2 in antiretroviral treatment-experienced HIV-1 infected adult subjects. A total of 462 subjects received the recommended dose of ISENTRESS 400 mg twice daily in combination with optimized background therapy (OBT) compared to 237 subjects taking placebo in combination with OBT. The median duration of therapy in these trials was 96 weeks for subjects receiving ISENTRESS and 38 weeks for subjects receiving placebo. The total exposure to ISENTRESS was 708 patient-years versus 244 patient-years on placebo. The rates of discontinuation due to adverse events were 4% in subjects receiving ISENTRESS and 5% in subjects receiving placebo.

Clinical ADRs were considered by investigators to be causally related to ISENTRESS + OBT or placebo + OBT. Clinical ADRs of moderate to severe intensity occurring in ≥2% of subjects treated with ISENTRESS and occurring at a higher rate compared to placebo are presented in Table 9.

Table 9: Adverse Drug Reactions [Includes adverse reactions at least possibly, probably, or definitely related to the drug.] of Moderate to Severe Intensity [Intensities are defined as follows: Moderate (discomfort enough to cause interference with usual activity); Severe (incapacitating with inability to work or do usual activity).] Occurring in ≥2% of Treatment-Experienced Adult Subjects Receiving ISENTRESS and at a Higher Rate Compared to Placebo (96 Week Analysis)
System Organ Class, Adverse Reactions | Randomized Studies BENCHMRK 1 and BENCHMRK 2
System Organ Class, Adverse Reactions | ISENTRESS 400 mg Twice Daily + OBT (n = 462) | Placebo + OBT (n = 237)
Nervous System Disorders
Headache | 2% | <1%
n=total number of subjects per treatment group.

Laboratory Abnormalities

The percentages of adult subjects treated with ISENTRESS 400 mg twice daily or placebo in Studies BENCHMRK 1 and BENCHMRK 2 with selected Grade 2 to 4 laboratory abnormalities representing a worsening Grade from baseline are presented in Table 10.

Table 10: Selected Grade 2 to 4 Laboratory Abnormalities Reported in Treatment-Experienced Subjects (96 Week Analysis)
 |  | Randomized Studies BENCHMRK 1 and BENCHMRK 2
Laboratory Parameter Preferred Term (Unit) | Limit | ISENTRESS 400 mg Twice Daily + OBT (N = 462) | Placebo + OBT (N = 237)
Hematology
Absolute neutrophil count (10^3/µL)
Grade 2 | 0.75 - 0.999 | 4% | 5%
Grade 3 | 0.50 - 0.749 | 3% | 3%
Grade 4 | <0.50 | 1% | <1%
Hemoglobin (gm/dL)
Grade 2 | 7.5 - 8.4 | 1% | 3%
Grade 3 | 6.5 - 7.4 | 1% | 1%
Grade 4 | <6.5 | <1% | 0%
Platelet count (10^3/µL)
Grade 2 | 50 - 99.999 | 3% | 5%
Grade 3 | 25 - 49.999 | 1% | <1%
Grade 4 | <25 | 1% | <1%
Blood chemistry
Fasting (non-random) serum glucose test (mg/dL)
Grade 2 | 126 - 250 | 10% | 7%
Grade 3 | 251 - 500 | 3% | 1%
Grade 4 | >500 | 0% | 0%
Total serum bilirubin
Grade 2 | 1.6 - 2.5 × ULN | 6% | 3%
Grade 3 | 2.6 - 5.0 × ULN | 3% | 3%
Grade 4 | >5.0 × ULN | 1% | 0%
Serum aspartate aminotransferase
Grade 2 | 2.6 - 5.0 × ULN | 9% | 7%
Grade 3 | 5.1 - 10.0 × ULN | 4% | 3%
Grade 4 | >10.0 × ULN | 1% | 1%
Serum alanine aminotransferase
Grade 2 | 2.6 - 5.0 × ULN | 9% | 9%
Grade 3 | 5.1 - 10.0 × ULN | 4% | 2%
Grade 4 | >10.0 × ULN | 1% | 2%
Serum alkaline phosphatase
Grade 2 | 2.6 - 5.0 × ULN | 2% | <1%
Grade 3 | 5.1 - 10.0 × ULN | <1% | 1%
Grade 4 | >10.0 × ULN | 1% | <1%
Serum pancreatic amylase test
Grade 2 | 1.6 - 2.0 × ULN | 2% | 1%
Grade 3 | 2.1 - 5.0 × ULN | 4% | 3%
Grade 4 | >5.0 × ULN | <1% | <1%
Serum lipase test
Grade 2 | 1.6 - 3.0 × ULN | 5% | 4%
Grade 3 | 3.1 - 5.0 × ULN | 2% | 1%
Grade 4 | >5.0 × ULN | 0% | 0%
Serum creatine kinase
Grade 2 | 6.0 - 9.9 × ULN | 2% | 2%
Grade 3 | 10.0 - 19.9 × ULN | 4% | 3%
Grade 4 | ≥20.0 × ULN | 3% | 1%
ULN = Upper limit of normal range

Less Common Adverse Reactions Observed in Treatment-Naïve and Treatment-Experienced Studies

The following ADRs occurred in <2% of treatment-naïve or treatment-experienced subjects receiving ISENTRESS or ISENTRESS HD in a combination regimen. These events have been included because of their seriousness, increased frequency compared with efavirenz or placebo, or investigator's assessment of potential causal relationship.

Gastrointestinal Disorders: abdominal pain, gastritis, dyspepsia, vomiting

General Disorders and Administration Site Conditions: asthenia

Hepatobiliary Disorders: hepatitis

Immune System Disorders: hypersensitivity

Infections and Infestations: genital herpes, herpes zoster

Psychiatric Disorders: depression (particularly in subjects with a pre-existing history of psychiatric illness), including suicidal ideation and behaviors

Renal and Urinary Disorders: nephrolithiasis, renal failure

Selected Adverse Events - Adults

In studies of ISENTRESS 400 mg twice daily, cancers were reported in treatment-experienced subjects who initiated ISENTRESS or placebo, both with OBT, and in treatment-naïve subjects who initiated ISENTRESS or efavirenz, both with emtricitabine (+) tenofovir disoproxil fumarate; several were recurrent. The types and rates of specific cancers were those expected in a highly immunodeficient population (many had CD4+ counts below 50 cells/mm^3 and most had prior AIDS diagnoses). The risk of developing cancer in these studies was similar in the group receiving ISENTRESS and the group receiving the comparator.

Grade 2-4 creatine kinase laboratory abnormalities were observed in subjects treated with ISENTRESS and ISENTRESS HD (see Tables 6 and 8). Myopathy and rhabdomyolysis have been reported with ISENTRESS. Use with caution in patients at increased risk of myopathy or rhabdomyolysis, such as patients receiving concomitant medications known to cause these conditions and patients with a history of rhabdomyolysis, myopathy or increased serum creatine kinase.

Rash occurred more commonly in treatment-experienced subjects receiving regimens containing ISENTRESS + darunavir/ritonavir compared to subjects receiving ISENTRESS without darunavir/ritonavir or darunavir/ritonavir without ISENTRESS. However, rash that was considered drug related occurred at similar rates for all three groups. These rashes were mild to moderate in severity and did not limit therapy; there were no discontinuations due to rash.

Patients with Co-existing Conditions - Adults

Patients Co-infected with Hepatitis B and/or Hepatitis C Virus

In Phase III studies of ISENTRESS, patients with chronic (but not acute) active hepatitis B and/or hepatitis C virus co-infection were permitted to enroll provided that baseline liver function tests did not exceed 5 times the upper limit of normal (ULN). In the treatment-experienced studies, BENCHMRK 1 and BENCHMRK 2, 16% of all patients (114/699) were co-infected; in the treatment-naïve studies, STARTMRK and ONCEMRK, 6% (34/563) and 3% (23/797), respectively, were co-infected. In general the safety profile of ISENTRESS in subjects with hepatitis B and/or hepatitis C virus co-infection was similar to that in subjects without hepatitis B and/or hepatitis C virus co-infection, although the rates of AST and ALT abnormalities were higher in the subgroup with hepatitis B and/or hepatitis C virus co-infection for all treatment groups.

At 96 weeks, in treatment-experienced subjects receiving ISENTRESS 400 mg twice daily, Grade 2 or higher laboratory abnormalities that represent a worsening Grade from baseline of AST, ALT or total bilirubin occurred in 29%, 34% and 13%, respectively, of co-infected subjects treated with ISENTRESS as compared to 11%, 10% and 9% of all other subjects treated with ISENTRESS. At 240 weeks, in treatment-naïve subjects receiving ISENTRESS 400 mg twice daily, Grade 2 or higher laboratory abnormalities that represent a worsening Grade from baseline of AST, ALT or total bilirubin occurred in 22%, 44% and 17%, respectively, of co-infected subjects treated with ISENTRESS as compared to 13%, 13% and 5% of all other subjects treated with ISENTRESS.

At 96 weeks, in treatment-naïve subjects receiving ISENTRESS HD 1200 mg (2 × 600 mg) once daily, Grade 2 or higher laboratory abnormalities that represent a worsening Grade from baseline of AST, ALT or total bilirubin occurred in 27%, 40% and 13%, respectively, of co-infected subjects treated with ISENTRESS HD 1200 mg once daily as compared to 7%, 5% and 3% of all other subjects treated with ISENTRESS HD 1200 mg once daily.

Pediatrics

2 to 18 Years of Age

ISENTRESS has been studied in 126 antiretroviral treatment-experienced HIV-1 infected children and adolescents 2 to 18 years of age, in combination with other antiretroviral agents in IMPAACT P1066 [see Use in Specific Populations (8.4) and Clinical Studies (14.4)]. Of the 126 patients, 96 received the recommended dose of ISENTRESS.

In these 96 children and adolescents, frequency, type and severity of drug related adverse reactions through Week 24 were comparable to those observed in adults.

One patient experienced drug related clinical adverse reactions of Grade 3 psychomotor hyperactivity, abnormal behavior and insomnia; one patient experienced a Grade 2 serious drug related allergic rash.

One patient experienced drug related laboratory abnormalities, Grade 4 AST and Grade 3 ALT, which were considered serious.

4 Weeks to Less than 2 Years of Age

ISENTRESS has also been studied in 26 HIV-1 infected infants and toddlers 4 weeks to less than 2 years of age, in combination with other antiretroviral agents in IMPAACT P1066 [see Use in Specific Populations (8.4) and Clinical Studies (14.4)].

In these 26 infants and toddlers, the frequency, type and severity of drug related adverse reactions through Week 48 were comparable to those observed in adults.

One patient experienced a Grade 3 serious drug related allergic rash that resulted in treatment discontinuation.

HIV-1 Exposed Neonates

Forty-two neonates were treated with ISENTRESS for up to 6 weeks from birth, and followed for a total of 24 weeks in IMPAACT P1110 [see Use in Specific Populations (8.4)]. There were no drug related clinical adverse reactions and three drug related laboratory adverse reactions (one case of transient Grade 4 neutropenia in a subject receiving zidovudine-containing regimen for prevention of mother to child transmission (PMTCT), and two bilirubin elevations (one each, Grade 1 and Grade 2) considered non-serious and not requiring specific therapy). The safety profile in neonates was generally similar to that observed in older patients treated with ISENTRESS. No clinically meaningful differences in the adverse event profile of neonates were observed when compared to adults.

6.2 Postmarketing Experience

The following adverse reactions have been identified during postapproval use of ISENTRESS. Because these reactions are reported voluntarily from a population of uncertain size, it is not always possible to reliably estimate their frequency or establish a causal relationship to drug exposure.

Blood and Lymphatic System Disorders: thrombocytopenia

Gastrointestinal Disorders: diarrhea

Hepatobiliary Disorders: hepatic failure (with and without associated hypersensitivity) in patients with underlying liver disease and/or concomitant medications

Musculoskeletal and Connective Tissue Disorders: rhabdomyolysis

Nervous System Disorders: cerebellar ataxia

Psychiatric Disorders: anxiety, paranoia

7 DRUG INTERACTIONS

7.1 Effect of Other Agents on the Pharmacokinetics of Raltegravir

Raltegravir is not a substrate of cytochrome P450 (CYP) enzymes. Based on in vivo and in vitro studies, raltegravir is eliminated mainly by metabolism via a UGT1A1-mediated glucuronidation pathway. Coadministration of ISENTRESS with drugs that inhibit UGT1A1 may increase plasma levels of raltegravir and coadministration of ISENTRESS with drugs that induce UGT1A1, such as rifampin, may reduce plasma levels of raltegravir (see Table 11).

Selected drug interactions are presented in Table 11 [see Clinical Pharmacology (12.3)]. In some cases, recommendations differ for ISENTRESS versus ISENTRESS HD.

Table 11: Selected Drug Interactions in Adults
Concomitant Drug Class: Drug Name | Effect on Concentration of Raltegravir | Clinical Comment for ISENTRESS | Clinical Comment for ISENTRESS HD
Metal-Containing Antacids
Aluminum and/or magnesium-containing antacids | ↓ | Coadministration or staggered administration is not recommended.
Calcium carbonate antacid | ↓ | No dose adjustment | Co-administration is not recommended
Other Agents
Rifampin | ↓ | The recommended dosage is 800 mg twice daily during coadministration with rifampin. There are no data to guide co-administration of ISENTRESS with rifampin in patients below 18 years of age [see Dosage and Administration (2.1)]. | Coadministration is not recommended.
Tipranavir/ritonavir |  | No dose adjustment | Coadministration is not recommended
Etravirine | ↓ | No dose adjustment | Coadministration is not recommended.
Strong inducers of drug metabolizing enzymes not mentioned above e.g., Carbamazepine Phenobarbital Phenytoin | ↓↔ | The impact of other strong inducers of drug metabolizing enzymes on raltegravir is unknown. Coadministration is not recommended.

7.2 Drugs without Clinically Significant Interactions with ISENTRESS or ISENTRESS HD

ISENTRESS

In drug interaction studies performed using ISENTRESS film-coated tablets 400 mg twice daily dose, raltegravir did not have a clinically meaningful effect on the pharmacokinetics of the following: ethinyl estradiol/norgestimate, methadone, midazolam, lamivudine, tenofovir disoproxil fumarate, etravirine, darunavir/ritonavir, or boceprevir. Moreover, atazanavir, atazanavir/ritonavir, boceprevir, calcium carbonate antacids, darunavir/ritonavir, efavirenz, etravirine, omeprazole, or tipranavir/ritonavir did not have a clinically meaningful effect on the pharmacokinetics of 400 mg twice daily raltegravir. No dose adjustment is required when ISENTRESS 400 mg twice daily is coadministered with these drugs.

There is no predicted pharmacokinetic drug interaction between ISENTRESS and tenofovir alafenamide.

ISENTRESS HD

In drug interaction studies, efavirenz did not have a clinically meaningful effect on the pharmacokinetics of ISENTRESS HD 1200 mg (2 × 600 mg) once daily. No dose adjustment is recommended when ISENTRESS HD 1200 mg once daily is coadministered with atazanavir, atazanavir/ritonavir, hormonal contraceptives, methadone, lamivudine, tenofovir disoproxil fumarate, darunavir/ritonavir, boceprevir, efavirenz and omeprazole.

There is no predicted pharmacokinetic drug interaction between ISENTRESS HD and tenofovir alafenamide.

8 USE IN SPECIFIC POPULATIONS

8.1 Pregnancy

Pregnancy Exposure Registry

There is a pregnancy exposure registry that monitors pregnancy outcomes in women. Healthcare providers are encouraged to register patients by calling the Antiretroviral Pregnancy Registry (APR) at 1-800-258-4263.

Risk Summary

Available data from the APR show no difference in the rate of overall birth defects for raltegravir compared to the background rate for major birth defects of 2.7% in the U.S. reference population of the Metropolitan Atlanta Congenital Defects Program (MACDP) (see Data). The rate of miscarriage is not reported in the APR. The estimated background rate of miscarriage in clinically recognized pregnancies in the U.S. general population is 15-20%. The background risk for major birth defects and miscarriage for the indicated population is unknown. Methodological limitations of the APR include the use of MACDP as the external comparator group. The MACDP population is not disease-specific, evaluates women and infants from a limited geographic area, and does not include outcomes for births that occurred at <20 weeks gestation (see Data).

In animal reproduction studies in rats and rabbits, no evidence of adverse developmental outcomes was observed with oral administration of raltegravir during organogenesis at doses that produced exposures up to approximately 4 times the maximum recommended human dose (MRHD) of 1200 mg (see Data).

Data

Human Data

Based on prospective reports from the APR of over 850 exposures to raltegravir during pregnancy resulting in live births (including over 450 exposures in the first trimester), there was no difference between the overall risk of birth defects for raltegravir compared with the background birth defect rate of 2.7% in the U.S. reference population of the MACDP. The prevalence of defects in live births was 3.1% (95% CI: 1.7% to 5.1%) following first trimester exposure to raltegravir-containing regimens and 3.7% (95% CI: 2.1% to 6.0%) following second and third trimester exposure to raltegravir-containing regimens.

There are limited data on the use of ISENTRESS 1200 mg (2 x 600 mg) once daily in pregnant women.

Animal Data

In a combined embryo/fetal and pre/postnatal development study, raltegravir was administered orally to rats at doses of 100, 300, 600 mg/kg/day on gestation day 6 to 20 or from gestation day 6 to lactation day 20. No effects on pre/postnatal development were observed up to the highest dose tested. Embryo-fetal findings were limited to an increase in the incidence of supernumerary ribs in the 600 mg/kg/day group. Systemic exposure (AUC) at 600 mg/kg/day was approximately 3 times higher than exposure at the MRHD of 1200 mg.

In pregnant rabbits, raltegravir was administered orally at doses of 100, 500, or 1000 mg/kg/day during the gestation days 7 to 20. No embryo/fetal effects were noted up to the highest dose of 1000 mg/kg/day. Systemic exposure (AUC) at 1000 mg/kg/day was approximately 4 times higher than exposures at the MRHD of 1200 mg. In both species, raltegravir has been shown to cross the placenta, with fetal plasma concentrations observed in rats approximately 1.5 to 2.5 times greater than in maternal plasma and fetal plasma concentrations in rabbits approximately 2% that of maternal concentrations on gestation day 20.

8.2 Lactation

Risk Summary

The Centers for Disease Control and Prevention recommend that HIV-1 infected mothers in the United States not breastfeed their infants to avoid risking postnatal transmission of HIV-1 infection. There are no data on the presence of raltegravir in human milk, the effects on the breastfed infant, or the effects on milk production. When administered to lactating rats, raltegravir was present in milk (see Data). Because of the potential for: 1) HIV transmission (in HIV-negative infants), 2) developing viral resistance (in HIV-positive infants), and 3) adverse reactions in a breastfed infant, instruct mothers not to breastfeed if they are receiving ISENTRESS/ISENTRESS HD.

Data

Raltegravir was excreted into the milk of lactating rats following oral administration (600 mg/kg/day) from gestation day 6 to lactation day 14, with milk concentrations approximately 3 times that of maternal plasma concentrations observed 2 hours postdose on lactation day 14.

8.4 Pediatric Use

ISENTRESS

HIV-1 Infected Children

The safety, tolerability, pharmacokinetic profile, and efficacy of twice daily ISENTRESS were evaluated in HIV-1 infected infants, children and adolescents 4 weeks to 18 years of age in an open-label, multicenter clinical trial, IMPAACT P1066 [see Dosage and Administration (2.3), Clinical Pharmacology (12.3) and Clinical Studies (14.4)]. The safety profile was comparable to that observed in adults [see Adverse Reactions (6.1)].

HIV-1 Exposed Neonates

The safety and pharmacokinetics of ISENTRESS for oral suspension were evaluated in 42 full-term HIV-1 exposed neonates at high risk of acquiring HIV-1 infection in a Phase 1, open-label, multicenter clinical study, IMPAACT P1110. Cohort 1 neonates received 2 single doses of ISENTRESS for oral suspension: the first within 48 hours of birth and the second at 7 to 10 days of age. Cohort 2 neonates received daily dosing of ISENTRESS for oral suspension for 6 weeks: 1.5 mg/kg once daily starting within 48 hours of birth through day 7 (week 1); 3 mg/kg twice daily on days 8 to 28 of age (weeks 2 to 4); and 6 mg/kg twice daily on days 29 to 42 of age (weeks 5 and 6). Sixteen neonates were enrolled in Cohort 1 (10 were exposed and 6 were unexposed to raltegravir in utero) and 26 in Cohort 2 (all unexposed to raltegravir in utero); all infants received a standard of care antiretroviral drug regimen for prevention of mother to child transmission. All enrolled neonates were followed for safety for a duration of 24 weeks. The 42 infants were 52% male, 69% Black and 12% Caucasian. HIV-1 status was assessed by nucleic acid test at birth, week 6 and week 24; all patients were HIV-1 negative at completion of the study. The safety profile was comparable to that observed in adults [see Adverse Reactions (6.1)].

ISENTRESS is not recommended in pre-term neonates or in pediatric patients weighing less than 2 kg.

ISENTRESS HD

ISENTRESS HD once daily has not been studied in pediatric patients. However population PK modeling and simulation support the use of 1200 mg (2 × 600 mg) once daily in pediatric patients weighing at least 40 kg [see Clinical Pharmacology (12.3)].

8.5 Geriatric Use

Clinical studies of ISENTRESS/ISENTRESS HD did not include sufficient numbers of subjects aged 65 and over to determine whether they respond differently from younger subjects. Other reported clinical experience has not identified differences in responses between the elderly and younger subjects. In general, dose selection for an elderly patient should be cautious, reflecting the greater frequency of decreased hepatic, renal, or cardiac function, and of concomitant disease or other drug therapy.

8.6 Use in Patients with Hepatic Impairment

No dosage adjustment of ISENTRESS is necessary for patients with mild to moderate (Child-Pugh A and B) hepatic impairment. No hepatic impairment study has been conducted with ISENTRESS HD and therefore administration in subjects with hepatic impairment is not recommended. The effect of severe hepatic impairment on the pharmacokinetics of raltegravir has not been studied [see Clinical Pharmacology (12.3)].

8.7 Use in Patients with Renal Impairment

No dosage adjustment of ISENTRESS or ISENTRESS HD is necessary in patients with any degree of renal impairment [see Clinical Pharmacology (12.3)]. The extent to which ISENTRESS may be dialyzable is unknown; therefore, dosing before a dialysis session should be avoided.

10 OVERDOSAGE

In the event of an overdose, it is reasonable to employ the standard supportive measures, e.g., remove unabsorbed material from the gastrointestinal tract, employ clinical monitoring (including obtaining an electrocardiogram), and institute supportive therapy if required. The extent to which ISENTRESS may be dialyzable is unknown.

11 DESCRIPTION

ISENTRESS contains raltegravir potassium, a human immunodeficiency virus integrase strand transfer inhibitor. The chemical name for raltegravir potassium is N-[(4-Fluorophenyl) methyl]-1,6-dihydro-5-hydroxy-1-methyl-2-[1-methyl-1-[[(5-methyl-1,3,4-oxadiazol-2-yl)carbonyl]amino]ethyl]-6-oxo-4-pyrimidinecarboxamide monopotassium salt.

The empirical formula is C20H20FKN6O5 and the molecular weight is 482.51. The structural formula is:

Raltegravir potassium is a white to off-white powder. It is soluble in water, slightly soluble in methanol, very slightly soluble in ethanol and acetonitrile and insoluble in isopropanol.

Each 400 mg film-coated tablet of ISENTRESS for oral administration contains 434.4 mg of raltegravir (as potassium salt), equivalent to 400 mg of raltegravir free phenol and the following inactive ingredients: calcium phosphate dibasic anhydrous, hypromellose 2208, lactose monohydrate, magnesium stearate, microcrystalline cellulose, poloxamer 407 (contains 0.01% butylated hydroxytoluene as antioxidant), sodium stearyl fumarate. In addition, the film coating contains the following inactive ingredients: black iron oxide, polyethylene glycol 3350, polyvinyl alcohol, red iron oxide, talc and titanium dioxide.

Each 600 mg film-coated tablet of ISENTRESS HD for oral administration contains 651.6 mg of raltegravir (as potassium salt), equivalent to 600 mg of raltegravir free phenol and the following inactive ingredients: croscarmellose sodium, hypromellose 2910, magnesium stearate, microcrystalline cellulose. The film coating contains the following inactive ingredients: ferrosoferric oxide, hypromellose 2910, iron oxide yellow, lactose monohydrate, triacetin and titanium dioxide. The tablet may also contain trace amount of carnauba wax.

Each 100 mg chewable tablet of ISENTRESS for oral administration contains 108.6 mg of raltegravir (as potassium salt), equivalent to 100 mg of raltegravir free phenol and the following inactive ingredients: ammonium hydroxide, crospovidone, ethylcellulose 20 cP, fructose, hydroxypropyl cellulose, hypromellose 2910/6cP, magnesium stearate, mannitol, medium chain triglycerides, monoammonium glycyrrhizinate, natural and artificial flavors (orange, banana, and masking that contains aspartame), oleic acid, PEG 400, red iron oxide, saccharin sodium, sodium citrate dihydrate, sodium stearyl fumarate, sorbitol, sucralose and yellow iron oxide.

Each 25 mg chewable tablet of ISENTRESS for oral administration contains 27.16 mg of raltegravir (as potassium salt), equivalent to 25 mg of raltegravir free phenol and the following inactive ingredients: ammonium hydroxide, crospovidone, ethylcellulose 20 cP, fructose, hydroxypropyl cellulose, hypromellose 2910/6cP, magnesium stearate, mannitol, medium chain triglycerides, monoammonium glycyrrhizinate, natural and artificial flavors (orange, banana, and masking that contains aspartame), oleic acid, PEG 400, saccharin sodium, sodium citrate dihydrate, sodium stearyl fumarate, sorbitol, sucralose and yellow iron oxide.

Each packet of ISENTRESS for oral suspension 100 mg, contains 108.6 mg of raltegravir (as potassium salt), equivalent to 100 mg of raltegravir free phenol and the following inactive ingredients: ammonium hydroxide, banana with other natural flavors, carboxymethylcellulose sodium, crospovidone, ethylcellulose 20 cP, fructose, hydroxypropyl cellulose, hypromellose 2910/6cP, macrogol/PEG 400, magnesium stearate, maltodextrin, mannitol, medium chain triglycerides, microcrystalline cellulose, monoammonium glycyrrhizinate, oleic acid, sorbitol, sucralose and sucrose.

12 CLINICAL PHARMACOLOGY

12.1 Mechanism of Action

Raltegravir is an HIV-1 antiviral drug [see Microbiology (12.4)].

12.2 Pharmacodynamics

In a monotherapy study raltegravir (400 mg twice daily) demonstrated rapid antiviral activity with mean viral load reduction of 1.66 log10 copies/mL by day 10.

Cardiac Electrophysiology

At a dose 1.33 times the maximum approved recommended dose (and peak concentrations 1.25-fold higher than the maximum approved dose), raltegravir does not prolong the QT interval or PR interval to any clinically relevant extent.

12.3 Pharmacokinetics

Adults

Absorption

Raltegravir, given 400 mg twice daily, is absorbed with a Tmax of approximately 3 hours postdose in the fasted state in healthy subjects. Raltegravir 1200 mg once daily is rapidly absorbed with median Tmax of ~1.5 to 2 hours in the fasted state.

Raltegravir increases dose proportionally (AUC and Cmax) or slightly less than dose proportionally (C12hr) over the dose range 100 mg to 1600 mg.

The absolute bioavailability of raltegravir has not been established. The chewable tablet and oral suspension have higher oral bioavailability compared to the 400 mg film-coated tablet.

Relative to the raltegravir 400 mg formulation, the raltegravir 600 mg formulation has higher relative bioavailability.

Steady-state is generally reached in 2 days, with little to no accumulation with multiple-dose administration for the 400 mg twice daily and 1200 once daily formulation.

Effect of Food on Oral Absorption

The food effect of various formulations are presented in Table 12.

Table 12: Effect of Food on the Pharmacokinetics of Raltegravir Formulations
 |  | PK parameter ratio (fed/fasted)
Formulation | Meal Type | AUC Ratio (90% CI) | Cmax Ratio (90% CI) | Cmin Ratio (90% CI)
400 mg twice daily | Low Fat | 0.54 (0.41-0.71) | 0.48 (0.35-0.67) | 0.86 (0.54-1.36)
 | Moderate Fat | 1.13 (0.85-1.49) | 1.05 (0.75-1.46) | 1.66 (1.04-2.64)
 | High Fat | 2.11 (1.60-2.80) | 1.96 (1.41-2.73) | 4.13 (2.60-6.57)
1200 mg once daily | Low Fat | 0.58 (0.46-0.74) | 0.48 (0.37-0.62) | 0.84 (0.63-1.10)
 | High Fat | 1.02 (0.86-1.21) | 0.72 (0.58-0.90) | 0.88 (0.66-1.18)
Chewable tablet | High Fat | 0.94 (0.78-1.14) | 0.38 (0.28-0.52) | 2.88 (2.21-3.75)
Oral suspension | The effect of food on oral suspension was not studied.
Low fat meal: 300 Kcal, 2.5 g fat
Moderate fat meal: 600 Kcal, 21 g fat
High fat meal: 825 Kcal, 52 g fat

Distribution

Raltegravir is approximately 83% bound to human plasma protein over the concentration range of 2 to 10 µM.

In one study of HIV-1 infected subjects who received raltegravir 400 mg twice daily, raltegravir was measured in the cerebrospinal fluid. In the study (n=18), the median cerebrospinal fluid concentration was 5.8% (range 1 to 53.5%) of the corresponding plasma concentration. This median proportion was approximately 3-fold lower than the free fraction of raltegravir in plasma. The clinical relevance of this finding is unknown.

Metabolism and Excretion

The apparent terminal half-life of raltegravir is approximately 9 hours, with a shorter α-phase half-life (~1 hour) accounting for much of the AUC. Following administration of an oral dose of radiolabeled raltegravir, approximately 51 and 32% of the dose was excreted in feces and urine, respectively. In feces, only raltegravir was present, most of which is likely derived from hydrolysis of raltegravir-glucuronide secreted in bile as observed in preclinical species. Two components, namely raltegravir and raltegravir-glucuronide, were detected in urine and accounted for approximately 9 and 23% of the dose, respectively. The major circulating entity was raltegravir and represented approximately 70% of the total radioactivity; the remaining radioactivity in plasma was accounted for by raltegravir-glucuronide. The major mechanism of clearance of raltegravir in humans is UGT1A1-mediated glucuronidation.

Table 13: Multiple-Dose Pharmacokinetic Parameters of Raltegravir Following the Administration of 400 mg Twice Daily and 1200 mg Once Daily in HIV-infected Subjects
Parameter | 400 mg BID Geometric Mean (%CV) N=6 | 1200 mg QD Geometric Mean (%CV) N=524
AUC (µM∙hr) | AUC0-12hr= 14.3 (88.6) | AUC0-24hr = 55.3 (41.5)
Cmax (µM) | 4.5 (128) | 15.7 (45.8)
Cmin (nM) | C12hr = 142 (63.8) | C24hr = 107 (97.5)

Special Populations

Pediatric

ISENTRESS

Two pediatric formulations were evaluated in healthy adult volunteers, where the chewable tablet and oral suspension were compared to the 400 mg tablet. The chewable tablet and oral suspension demonstrated higher oral bioavailability, thus higher AUC, compared to the 400 mg tablet. In the same study, the oral suspension resulted in higher oral bioavailability compared to the chewable tablet. These observations resulted in proposed pediatric doses targeting 6 mg/kg/dose for the chewable tablets and oral suspension. As displayed in Table 14, the doses recommended for HIV-infected infants, children and adolescents 4 weeks to 18 years of age [see Dosage and Administration (2.3)] resulted in a pharmacokinetic profile of raltegravir similar to that observed in adults receiving 400 mg twice daily.

Overall, dosing in pediatric patients achieved exposures (Ctrough) above 45 nM in the majority of subjects, but some differences in exposures between formulations were observed. Pediatric patients above 25 kg administered the chewable tablets had lower trough concentrations (113 nM) compared to pediatric patients above 25 kg administered the 400 mg tablet formulation (233 nM) [see Clinical Studies (14.4)]. As a result, the 400 mg film-coated tablet is the recommended dose in patients weighing at least 25 kg; however, the chewable tablet offers an alternative regimen in patients weighing at least 25 kg who are unable to swallow the film-coated tablet [see Dosage and Administration (2.3)]. In addition, pediatric patients weighing 11 to 25 kg who were administered the chewable tablets had the lowest trough concentrations (82 nM) compared to all other pediatric subgroups.

Table 14: Raltegravir Steady-State Pharmacokinetic Parameters in Pediatric Patients Following Administration of Recommended Twice Daily Doses
Body Weight | Formulation | Dose | N [Number of patients with intensive pharmacokinetic (PK) results at the final recommended dose.] | Geometric Mean (%CV [Geometric coefficient of variation.]) AUC0-12hr (µM∙hr) | Geometric Mean (%CV) C12hr (nM)
≥25 kg | Film-coated tablet | 400 mg twice daily | 18 | 14.1 (121%) | 233 (157%)
≥25 kg | Chewable tablet | Weight-based dosing, see Table 3 | 9 | 22.1 (36%) | 113 (80%)
11 to less than 25 kg | Chewable tablet | Weight-based dosing, see Table 4 | 13 | 18.6 (68%) | 82 (123%)
3 to less than 20 kg | Oral suspension | Weight-based dosing, see Table 4 | 19 | 24.5 (43%) | 113 (69%)

Elimination of raltegravir in vivo in human is primarily through the UGT1A1-mediated glucuronidation pathway. UGT1A1 catalytic activity is negligible at birth and matures after birth. The dose recommended for neonates less than 4 weeks of age takes into consideration the rapidly increasing UGT1A1 activity and drug clearance from birth to 4 weeks of age. Table 15 displays pharmacokinetic parameters for neonates receiving the granules for oral suspension at the recommended dose [see Dosage and Administration (2.3)].

Table 15: Raltegravir Pharmacokinetic Parameters from IMPAACT P1110 Following Age and Weight-Based Dosing of Oral Suspension
Age (hours/days) at PK Sampling | Dose (See Table 5) | N [Number of patients with intensive pharmacokinetic (PK) results at the final recommended dose.] | Geometric Mean (%CV [Geometric coefficient of variation.]) AUC (μM∙hr) | Geometric Mean (%CV) Ctrough (nM)
Birth – 48 hours | 1.5 mg/kg once daily | 25 | 85.9 (38.4%) [AUC0-24hr (N = 24) and C24hr] | 2132.9 (64.2%)
15 to 18 days | 3.0 mg/kg twice daily | 23 | 32.2 (43.3%) [AUC0-12hr and C12hr] | 1255.5 (83.7%)

ISENTRESS HD

ISENTRESS HD 1200 mg (2 × 600 mg) was not evaluated in a pediatric clinical study. Exposures for pediatric subjects weighing at least 40 kg administered ISENTRESS HD are predicted to be comparable to adult exposures observed from Phase III ONCEMRK.

Age/Race/Gender

There is no clinically meaningful effect of age (18 years and older), race, or gender on the pharmacokinetics of raltegravir.

Hepatic Impairment

Raltegravir is eliminated primarily by glucuronidation in the liver. The pharmacokinetics of a single 400-mg dose of raltegravir were not altered in patients with moderate (Child-Pugh Score 7 to 9) hepatic impairment.

No hepatic impairment study has been conducted with ISENTRESS HD 1200 mg (2 × 600 mg) once daily. The effect of severe hepatic impairment on the pharmacokinetics of raltegravir has not been studied.

Renal Impairment

Renal clearance of unchanged drug is a minor pathway of elimination. The pharmacokinetics of a single 400-mg dose of raltegravir were not altered in patients with severe (24-hour creatinine clearance of <30 mL/min/1.73 m^2) renal impairment.

No renal impairment study was conducted with ISENTRESS HD 1200 mg (2 × 600 mg) once daily.

The extent to which ISENTRESS may be dialyzable is unknown.

Drug Interactions

In vitro, raltegravir does not inhibit (IC50>100 µM) CYP1A2, CYP2B6, CYP2C8, CYP2C9, CYP2C19, CYP2D6 or CYP3A. In vivo, raltegravir does not inhibit CYP3A4. Moreover, in vitro, raltegravir did not induce CYP1A2, CYP2B6 or CYP3A4. Similarly, raltegravir is not an inhibitor (IC50>50 µM) of UGT1A1 or UGT2B7, and raltegravir does not inhibit P-glycoprotein-mediated transport.

Raltegravir drug interaction study results are shown in Tables 16 and 17. For information regarding clinical recommendations [see Drug Interactions (7)].

Table 16: Effect of Other Agents on the Pharmacokinetics of Raltegravir in Adults
Coadministered Drug | Coadministered Drug Dose/Schedule | Raltegravir Dose/Schedule | Ratio (90% Confidence Interval) of Raltegravir Pharmacokinetic Parameters with/without Coadministered Drug; No Effect = 1.00
 |  |  | n | Cmax | AUC | Cmin
aluminum and magnesium hydroxide antacid [Study conducted in HIV-infected subjects.] | 20 mL single dose given with raltegravir | 400 mg twice daily | 25 | 0.56 (0.42, 0.73) | 0.51 (0.40, 0.65) | 0.37 (0.29, 0.48)
 | 20 mL single dose given 2 hours before raltegravir |  | 23 | 0.49 (0.33, 0.71) | 0.49 (0.35, 0.67) | 0.44 (0.34, 0.55)
 | 20 mL single dose given 2 hours after raltegravir |  | 23 | 0.78 (0.53, 1.13) | 0.70 (0.50, 0.96) | 0.43 (0.34, 0.55)
 | 20 mL single dose given 4 hours before raltegravir |  | 17 | 0.78 (0.55, 1.10) | 0.81 (0.63, 1.05) | 0.40 (0.31, 0.52)
 | 20 mL single dose given 4 hours after raltegravir |  | 18 | 0.70 (0.48, 1.04) | 0.68 (0.50, 0.92) | 0.38 (0.30, 0.49)
 | 20 mL single dose given 6 hours before raltegravir |  | 16 | 0.90 (0.58, 1.40) | 0.87 (0.64, 1.18) | 0.50 (0.39, 0.65)
 | 20 mL single dose given 6 hours after raltegravir |  | 16 | 0.90 (0.58, 1.41) | 0.89 (0.64, 1.22) | 0.51 (0.40, 0.64)
aluminum and magnesium hydroxide antacid | 20 mL single dose given 12 hours after raltegravir | 1200 mg single dose | 19 | 0.86 (0.65, 1.15) | 0.86 (0.73, 1.03) | 0.42 (0.34, 0.52)
atazanavir | 400 mg daily | 100 mg single dose | 10 | 1.53 (1.11, 2.12) | 1.72 (1.47, 2.02) | 1.95 (1.30, 2.92)
atazanavir | 400 mg daily | 1200 mg single dose | 14 | 1.16 (1.01, 1.33) | 1.67 (1.34, 2.10) | 1.26 (1.08, 1.46)
atazanavir/ritonavir | 300 mg/100 mg daily | 400 mg twice daily | 10 | 1.24 (0.87, 1.77) | 1.41 (1.12, 1.78) | 1.77 (1.39, 2.25)
boceprevir | 800 mg three times daily | 400 mg single dose | 22 | 1.11 (0.91, 1.36) | 1.04 (0.88, 1.22) | 0.75 (0.45, 1.23)
calcium carbonate antacid | 3000 mg single dose given with raltegravir | 400 mg twice daily | 24 | 0.48 (0.36, 0.63) | 0.45 (0.35, 0.57) | 0.68 (0.53, 0.87)
calcium carbonate antacid | 3000 mg single dose given with raltegravir | 1200 mg single dose | 19 | 0.26 (0.21, 0.32) | 0.28 (0.24, 0.32) | 0.52 (0.45, 0.61)
 | 3000 mg single dose given 12 hours after raltegravir |  |  | 0.98 (0.81, 1.17) | 0.90 (0.80, 1.03) | 0.43 (0.36, 0.51)
efavirenz | 600 mg daily | 400 mg single dose | 9 | 0.64 (0.41, 0.98) | 0.64 (0.52, 0.80) | 0.79 (0.49, 1.28)
efavirenz | 600 mg daily | 1200 mg single dose | 21 | 0.91 (0.70, 1.17) | 0.86 (0.73, 1.01) | 0.94 (0.76, 1.17)
etravirine | 200 mg twice daily | 400 mg twice daily | 19 | 0.89 (0.68, 1.15) | 0.90 (0.68, 1.18) | 0.66 (0.34, 1.26)
omeprazole | 20 mg daily | 400 mg twice daily | 18 | 1.51 (0.98, 2.35) | 1.37 (0.99, 1.89) | 1.24 (0.95, 1.62)
rifampin | 600 mg daily | 400 mg single dose | 9 | 0.62 (0.37, 1.04) | 0.60 (0.39, 0.91) | 0.39 (0.30, 0.51)
rifampin | 600 mg daily | 400 mg twice daily when administered alone; 800 mg twice daily when administered with rifampin | 14 | 1.62 (1.12, 2.33) | 1.27 (0.94, 1.71) | 0.47 (0.36, 0.61)
ritonavir | 100 mg twice daily | 400 mg single dose | 10 | 0.76 (0.55, 1.04) | 0.84 (0.70, 1.01) | 0.99 (0.70, 1.40)
tenofovir disoproxil fumarate | 300 mg daily | 400 mg twice daily | 9 | 1.64 (1.16, 2.32) | 1.49 (1.15, 1.94) | 1.03 (0.73, 1.45)
tipranavir/ritonavir | 500 mg/200 mg twice daily | 400 mg twice daily | 15 (14 for Cmin) | 0.82 (0.46, 1.46) | 0.76 (0.49, 1.19) | 0.45 (0.31, 0.66)

Table 17: Effect of Raltegravir on the Pharmacokinetics of Other Agents in Adults
Substrate Drug | Raltegravir Dose/Schedule | Ratio (90% Confidence Interval) of Substrate Pharmacokinetic Parameters with/without Coadministered Drug; No Effect = 1.00
Substrate Drug | Raltegravir Dose/Schedule | n | Cmax | AUC | Cmin
Tenofovir disoproxil fumarate 300 mg | 400 mg | 9 | 0.77 (0.69, 0.85) | 0.90 (0.82, 0.99) | C24hr 0.87 (0.74, 1.02)
Etravirine 200 mg | 400 mg | 19 | 1.04 (0.97, 1.12) | 1.10 (1.03, 1.16) | 1.17 (1.10, 1.26)

In drug interaction studies, there was no effect of raltegravir on the PK of ethinyl estradiol, methadone, midazolam or boceprevir.

12.4 Microbiology

Mechanism of Action

Raltegravir inhibits the catalytic activity of HIV-1 integrase, an HIV-1 encoded enzyme that is required for viral replication. Inhibition of integrase prevents the covalent insertion, or integration, of unintegrated linear HIV-1 DNA into the host cell genome preventing the formation of the HIV-1 provirus. The provirus is required to direct the production of progeny virus, so inhibiting integration prevents propagation of the viral infection. Raltegravir did not significantly inhibit human phosphoryltransferases including DNA polymerases α, β, and γ.

Antiviral Activity in Cell Culture

Raltegravir at concentrations of 31 ± 20 nM resulted in 95% inhibition (EC95) of viral spread (relative to an untreated virus-infected culture) in human T-lymphoid cell cultures infected with the cell-line adapted HIV-1 variant H9IIIB. In addition, 5 clinical isolates of HIV-1 subtype B had EC95 values ranging from 9 to 19 nM in cultures of mitogen-activated human peripheral blood mononuclear cells. In a single-cycle infection assay, raltegravir inhibited infection of 23 HIV-1 isolates representing 5 non-B subtypes (A, C, D, F, and G) and 5 circulating recombinant forms (AE, AG, BF, BG, and cpx) with EC50 values ranging from 5 to 12 nM. Raltegravir also inhibited replication of an HIV-2 isolate when tested in CEMx174 cells (EC95 value = 6 nM). No antagonism was observed when human T-lymphoid cells infected with the H9IIIB variant of HIV-1 were incubated with raltegravir in combination with non-nucleoside reverse transcriptase inhibitors (delavirdine, efavirenz, or nevirapine); nucleoside analog reverse transcriptase inhibitors (abacavir, didanosine, lamivudine, stavudine, tenofovir, or zidovudine); protease inhibitors (amprenavir, atazanavir, indinavir, lopinavir, nelfinavir, ritonavir, or saquinavir); or the entry inhibitor enfuvirtide.

Resistance

The mutations observed in the HIV-1 integrase coding sequence that contributed to raltegravir resistance (evolved either in cell culture or in subjects treated with raltegravir) generally included an amino acid substitution at either Y143 (changed to C, H, or R) or Q148 (changed to H, K, or R) or N155 (changed to H) plus one or more additional substitutions (i.e., L74M, E92Q, Q95K/R, T97A, E138A/K, G140A/S, V151I, G163R, H183P, Y226C/D/F/H, S230R, and D232N). E92Q, T97A, and F121C are occasionally seen in the absence of substitutions at Y143, Q148, or N155 in raltegravir treatment-failure subjects.

Treatment-Naïve Adult Subjects: By Week 240 in the STARTMRK trial, the primary raltegravir resistance-associated substitutions were observed in 4 (2 with Y143H/R and 2 with Q148H/R) of the 12 virologic failure subjects with evaluable genotypic data from paired baseline and raltegravir treatment-failure isolates. By Week 96 in the ONCEMRK trial, primary raltegravir resistance substitutions were observed in on treatment isolates obtained from 4 (3 with N155H and 1 with E92Q) of 14 virologic failure subjects with evaluable genotypic data in the 1200 mg QD arm and 2 (1 with N155H and 1 with T97A) of 6 virologic failure subjects in the 400 mg BID arm. Additional integrase substitutions observed included L74M, Q95K, V151I, E170A, I203M and D232N. These resistant isolates exhibited 6.2- to 19-fold reductions in susceptibility to raltegravir. Overall, at Week 96, detection of raltegravir resistance was not different between the QD and BID arms in subjects who were failing treatment and had resistance data evaluable (28.6% versus 33.3%, respectively).

Treatment-Experienced Adult Subjects: By Week 96 in the BENCHMRK trials, at least one of the primary raltegravir resistance-associated substitutions, Y143C/H/R, Q148H/K/R, and N155H, was observed in 76 of the 112 virologic failure subjects with evaluable genotypic data from paired baseline and raltegravir treatment-failure isolates. The emergence of the primary raltegravir resistance-associated substitutions was observed cumulatively in 70 subjects by Week 48 and 78 subjects by Week 96, 15.2% and 17% of the raltegravir recipients, respectively. Some (n=58) of those HIV-1 isolates harboring one or more of the primary raltegravir resistance-associated substitutions were evaluated for raltegravir susceptibility yielding a median decrease of 26.3-fold (mean 48.9 ± 44.8-fold decrease, ranging from 0.8- to 159-fold) compared to the wild-type reference.

Cross Resistance

Cross resistance has been observed among HIV-1 integrase strand transfer inhibitors (INSTIs). Amino acid substitutions in HIV-1 integrase conferring resistance to raltegravir generally also confer resistance to elvitegravir. Substitutions at amino acid Y143 confer greater reductions in susceptibility to raltegravir than to elvitegravir, and the E92Q substitution confers greater reductions in susceptibility to elvitegravir than to raltegravir. Viruses harboring a substitution at amino acid Q148, along with one or more other raltegravir resistance substitutions, may also have clinically significant resistance to dolutegravir.

12.5 Pharmacogenomics

UGT1A1 Polymorphism

There is no evidence that common UGT1A1 polymorphisms alter raltegravir pharmacokinetics to a clinically meaningful extent. In a comparison of 30 adult subjects with *28/*28 genotype (associated with reduced activity of UGT1A1) to 27 adult subjects with wild-type genotype, the geometric mean ratio (90% CI) of AUC was 1.41 (0.96, 2.09).

In the neonatal study IMPAACT P1110, there was no association between apparent clearance (CL/F) of raltegravir and UGT1A1 genotype polymorphisms.

13 NONCLINICAL TOXICOLOGY

13.1 Carcinogenesis, Mutagenesis, Impairment of Fertility

Carcinogenicity studies of raltegravir in mice did not show any carcinogenic potential. At the highest dose levels, 400 mg/kg/day in females and 250 mg/kg/day in males, systemic exposure was 1.8-fold (females) or 1.2-fold (males) greater than the AUC (54 µM∙hr) at the 400-mg twice daily human dose. Treatment-related squamous cell carcinoma of nose/nasopharynx was observed in female rats dosed with 600 mg/kg/day raltegravir for 104 weeks. These tumors were possibly the result of local irritation and inflammation due to local deposition and/or aspiration of drug in the mucosa of the nose/nasopharynx during dosing. No tumors of the nose/nasopharynx were observed in rats dosed with 150 mg/kg/day (males) and 50 mg/kg/day (females) and the systemic exposure in rats was 1.7-fold (males) to 1.4-fold (females) greater than the AUC (54 µM∙hr) at the 400-mg twice daily human dose.

No evidence of mutagenicity or genotoxicity was observed in in vitro microbial mutagenesis (Ames) tests, in vitro alkaline elution assays for DNA breakage, and in vitro and in vivo chromosomal aberration studies.

No effect on fertility was seen in male and female rats at doses up to 600 mg/kg/day which resulted in a 3-fold exposure above the exposure at the recommended human dose.

14 CLINICAL STUDIES

14.1 Description of Clinical Studies

The evidence of durable efficacy of ISENTRESS 400 mg twice daily is based on the analyses of 240-week data from a randomized, double-blind, active-controlled trial, STARTMRK evaluating ISENTRESS 400 mg twice daily in antiretroviral treatment-naïve HIV-1 infected adult subjects, the analysis of 96-week data from a randomized, double-blind, active-control trial, ONCEMRK evaluating ISENTRESS HD 1200 mg (2 × 600 mg) once daily in treatment-naïve adult subjects, and 96-week data from 2 randomized, double-blind, placebo-controlled studies, BENCHMRK 1 and BENCHMRK 2, evaluating ISENTRESS 400 mg twice daily in antiretroviral treatment-experienced HIV-1 infected adult subjects. See Table 18.

Table 18: Trials Conducted with ISENTRESS and ISENTRESS HD in Subjects with HIV-1 Infection
Trial | Study Type | Population | Study Arms (N) | Dose/Formulation | Timepoint
STARTMRK | Randomized, double-blind, active-controlled | Treatment-Naïve Adults | ISENTRESS 400 mg Twice Daily (281) Efavirenz 600 mg At Bedtime (282) Both in combination with emtricitabine (+) tenofovir disoproxil fumarate | 400 mg film-coated tablet | Week 240
ONCEMRK | Randomized, double-blind, active-controlled | Treatment-Naïve Adults | ISENTRESS HD 1200 mg Once Daily (531) | 600 mg film-coated tablet | Week 96
 |  |  | ISENTRESS 400 mg Twice Daily (266) Both in combination with emtricitabine (+) tenofovir disoproxil fumarate | 400 mg film-coated tablet
BENCHMRK 1 | Randomized, double-blind, placebo-controlled | Treatment-Experienced Adults | ISENTRESS 400 mg Twice Daily (232) Placebo (118) Both in combination with optimized background therapy | 400 mg film-coated tablet | Week 240 (Week 156 on double-blind plus Week 84 on open-label)
BENCHMRK 2 | Randomized, double-blind, placebo-controlled | Treatment-Experienced Adults | ISENTRESS 400 mg Twice Daily (230) Placebo (119) Both in combination with optimized background therapy | 400 mg film-coated tablet | Week 240 (Week 156 on double-blind plus Week 84 on open-label)
IMPAACT P1066 | Open-label, non-comparative | Pediatric Patients – 4 weeks to 18 years of age (Treatment-Experienced or Failed Prior PMTCT) | ISENTRESS 400 mg tablet Twice Daily – 12 to 18 years or 6 to <12 years and ≥25 kg (87) ISENTRESS chewable tablet- Weight-Based Dose to Approximate 6 mg/kg Twice Daily – 2 to <12 years (39) ISENTRESS for oral suspension- Weight-Based Dose to Approximate 6 mg/kg Twice Daily – 4 weeks to <2 years (26) In combination with optimized background therapy | 400 mg film-coated tablet 25 mg and 100 mg chewable tablet 100 mg sachet for oral suspension | Week 240

14.2 Treatment-Naïve Adult Subjects

STARTMRK (ISENTRESS 400 mg twice daily)

STARTMRK is a Phase 3 randomized, international, double-blind, active-controlled trial to evaluate the safety and efficacy of ISENTRESS 400 mg twice daily versus efavirenz 600 mg at bedtime both with emtricitabine (+) tenofovir disoproxil fumarate in treatment-naïve HIV-1-infected subjects with HIV-1 RNA >5000 copies/mL. Randomization was stratified by screening HIV-1 RNA level (≤50,000 copies/mL; or >50,000 copies/mL) and by hepatitis status. In STARTMRK, 563 subjects were randomized and received at least 1 dose of either raltegravir 400 mg twice daily or efavirenz 600 mg at bedtime, both in combination with emtricitabine (+) tenofovir disoproxil fumarate. There were 563 subjects included in the efficacy and safety analyses. At baseline, the median age of subjects was 37 years (range: 19-71), 19% female, 58% non-white, 6% had hepatitis B and/or C virus co-infection, 20% were CDC Class C (AIDS), 53% had HIV-1 RNA greater than 100,000 copies per mL, and 47% had CD4+ cell count less than 200 cells per mm^3; the frequencies of these baseline characteristics were similar between treatment groups.

ONCEMRK (ISENTRESS HD 1200 mg [2 × 600 mg] once daily)

ONCEMRK is a Phase 3 randomized, international, double-blind, active-controlled trial to evaluate the safety and efficacy of ISENTRESS HD 1200 mg (2 × 600 mg) once daily versus ISENTRESS 400 mg twice daily, both in combination with emtricitabine (+) tenofovir disoproxil fumarate, in treatment-naïve HIV-1-infected subjects with HIV-1 RNA ≥1000 copies/mL. Randomization was stratified by screening HIV-1 RNA level (≤100,000 or >100,000 copies/mL) and by hepatitis B and C infection status.

In ONCEMRK, 797 subjects were randomized and received at least 1 dose of either raltegravir 1200 mg once daily or raltegravir 400 mg twice daily, both in combination with emtricitabine (+) tenofovir disoproxil fumarate. There were 797 subjects included in the efficacy and safety analyses. At baseline, the median age of subjects was 34 years (range: 18-84), 15% female, 41% non-white, 3% had hepatitis B and/or C virus co-infection, 13% were CDC Class C (AIDS), 28% had HIV-1 RNA greater than 100,000 copies per mL, and 13% had CD4+ cell count less than 200 cells per mm^3; the frequencies of these baseline characteristics were similar between treatment groups.

Table 19 shows the virologic outcomes in both studies. Side-by-side tabulation is to simplify presentation; direct comparisons across trials should not be made due to differing duration of follow-up.

Table 19: Virologic Outcomes of Randomized Treatment in STARTMRK and ONCEMRK (Snapshot Algorithm) in HIV Treatment-Naïve Adults
 | STARTMRK Week 240 |  | ONCEMRK Week 96
 | ISENTRESS 400 mg Twice Daily (N=281) | Efavirenz 600 mg At Bedtime (N=282) | ISENTRESS HD 1200 mg Once Daily (N=531) | ISENTRESS 400 mg Twice Daily (N=266)
HIV RNA < Lower Limit of Quantitation [Lower Limit of Quantitation: STARTMRK <50 copies/mL; ONCEMRK < 40 copies/mL.] | 66% | 60% | 82% | 80%
Treatment Difference | 6.6% (95% CI: -1.4%, 14.5%) |  | 1.4% (95% CI: -4.4%, 7.3%)
HIV RNA ≥ Lower Limit of Quantitation | 8% | 15% | 9% | 8%
No Virologic Data at Analysis Timepoint | 26% | 26% | 9% | 12%
Reasons
Discontinued trial due to AE or Death [Includes subjects who discontinued because of adverse event (AE) or death at any time point from day 1 through the time window if this resulted in no virologic data on treatment during the specified window.] | 5% | 10% | 1% | 3%
Discontinued trial for Other Reasons [Other Reasons includes: lost to follow-up, moved, non-compliance with study drug, physician decision, pregnancy, withdrawal by subject.] | 15% | 14% | 7% | 8%
On trial but missing data at timepoint | 6% | 2% | 1% | 2%
Notes: ISENTRESS BID, ISENTRESS HD and Efavirenz were administered with emtricitabine (+) tenofovir disoproxil fumarate

In the ONCEMRK trial, ISENTRESS HD 1200 mg (2 × 600 mg) once daily demonstrated consistent virologic and immunologic efficacy relative to ISENTRESS 400 mg twice daily, both in combination with emtricitabine (+) tenofovir disoproxil fumarate, across demographic and baseline prognostic factors, including: baseline HIV RNA levels >100,000 copies/mL and demographic groups (including age, gender, race, ethnicity and region), concomitant proton pump inhibitors/H2 blockers use and viral subtypes (comparing non-clade B as a group to clade B).

Consistent efficacy in subjects receiving ISENTRESS HD 1200 mg (2 × 600 mg) once daily was observed across HIV subtypes with 80.6% (270/335) and 83.5% (162/194) of subjects with B and non-B subtypes respectively, achieving HIV RNA <40 copies/mL at week 96 (Snapshot approach).

14.3 Treatment-Experienced Adult Subjects

BENCHMRK 1 and BENCHMRK 2 are Phase 3 studies to evaluate the safety and antiretroviral activity of ISENTRESS 400 mg twice daily in combination with an optimized background therapy (OBT), versus OBT alone, in HIV-1-infected subjects, 16 years or older, with documented resistance to at least 1 drug in each of 3 classes (NNRTIs, NRTIs, PIs) of antiretroviral therapies. Randomization was stratified by degree of resistance to PI (1PI vs. >1PI) and the use of enfuvirtide in the OBT. Prior to randomization, OBT was selected by the investigator based on genotypic/phenotypic resistance testing and prior ART history.

Table 20 shows the demographic characteristics of subjects in the group receiving ISENTRESS 400 mg twice daily and subjects in the placebo group.

Table 20: Trials BENCHMRK 1 and BENCHMRK 2 Baseline Characteristics
Randomized Studies BENCHMRK 1 and BENCHMRK 2 | ISENTRESS 400 mg Twice Daily + OBT (N = 462) | Placebo + OBT (N = 237)
Gender
Male | 88% | 89%
Female | 12% | 11%
Race
White | 65% | 73%
Black | 14% | 11%
Asian | 3% | 3%
Hispanic | 11% | 8%
Others | 6% | 5%
Age (years)
Median (min, max) | 45 (16 to 74) | 45 (17 to 70)
CD4+ Cell Count
Median (min, max), cells/mm^3 | 119 (1 to 792) | 123 (0 to 759)
≤50 cells/mm^3 | 32% | 33%
>50 and ≤200 cells/mm^3 | 37% | 36%
Plasma HIV-1 RNA
Median (min, max), log10 copies/mL | 4.8 (2 to 6) | 4.7 (2 to 6)
>100,000 copies/mL | 36% | 33%
History of AIDS
Yes | 92% | 91%
Prior Use of ART, Median (1st Quartile, 3rd Quartile)
Years of ART Use | 10 (7 to 12) | 10 (8 to 12)
Number of ART | 12 (9 to 15) | 12 (9 to 14)
Hepatitis Co-infection [Hepatitis B virus surface antigen positive or hepatitis C virus antibody positive.]
No Hepatitis B or C virus | 83% | 84%
Hepatitis B virus only | 8% | 3%
Hepatitis C virus only | 8% | 12%
Co-infection of Hepatitis B and C virus | 1% | 1%
Stratum
Enfuvirtide in OBT | 38% | 38%
Resistant to ≥2 PI | 97% | 95%

Table 21 compares the characteristics of optimized background therapy at baseline in the group receiving ISENTRESS 400 mg twice daily and subjects in the control group.

Table 21: Trials BENCHMRK 1 and BENCHMRK 2 Characteristics of Optimized Background Therapy at Baseline
Randomized Studies BENCHMRK 1 and BENCHMRK 2 | ISENTRESS 400 mg Twice Daily + OBT (N = 462) | Placebo + OBT (N = 237)
Number of ARTs in OBT
Median (min, max) | 4 (1 to 7) | 4 (2 to 7)
Number of Active PI in OBT by Phenotypic Resistance Test [Darunavir use in OBT in darunavir-naïve subjects was counted as one active PI.]
0 | 36% | 41%
1 or more | 60% | 58%
Phenotypic Sensitivity Score (PSS) [The Phenotypic Sensitivity Score (PSS) and the Genotypic Sensitivity Score (GSS) were defined as the total oral ARTs in OBT to which a subject's viral isolate showed phenotypic sensitivity and genotypic sensitivity, respectively, based upon phenotypic and genotypic resistance tests. Enfuvirtide use in OBT in enfuvirtide-naïve subjects was counted as one active drug in OBT in the GSS and PSS. Similarly, darunavir use in OBT in darunavir-naïve subjects was counted as one active drug in OBT.]
0 | 15% | 18%
1 | 31% | 30%
2 | 31% | 28%
3 or more | 18% | 20%
Genotypic Sensitivity Score (GSS)
0 | 25% | 27%
1 | 38% | 40%
2 | 24% | 21%
3 or more | 11% | 10%

Week 96 outcomes for the 699 subjects randomized and treated with the recommended dose of ISENTRESS 400 mg twice daily or placebo in the pooled BENCHMRK 1 and 2 studies are shown in Table 22.

Table 22: Virologic Outcomes of Randomized Treatment of BENCHMRK 1 and BENCHMRK 2 Trials at 96 Weeks (Pooled Analysis)
 | ISENTRESS 400 mg Twice Daily + OBT (N = 462) | Placebo + OBT (N = 237)
Subjects with HIV-1 RNA less than 50 copies/mL | 55% | 27%
Virologic Failure [Includes subjects who switched to open-label raltegravir after Week 16 due to the protocol-defined virologic failure, subjects who discontinued prior to Week 96 for lack of efficacy, subjects changed OBT due to lack of efficacy prior to Week 96, or subjects who were ≥50 copies in the 96 week window.] | 35% | 66%
No virologic data at Week 96 Window
Reasons
Discontinued study due to AE or death [Includes subjects who discontinued due to AE or death at any time point from day 1 through the Week 96 window if this resulted in no virologic data on treatment during the Week 96 window.] | 3% | 3%
Discontinued study for other reasons [Other includes: withdrew consent, loss to follow-up, moved etc., if the viral load at the time of discontinuation was <50 copies/mL.] | 4% | 4%
Missing data during window but on study | 4% | <1%

The mean changes in CD4 count from baseline were 118 cells/mm^3 in the group receiving ISENTRESS 400 mg twice daily and 47 cells/mm^3 for the control group.

Treatment-emergent CDC Category C events occurred in 4% of the group receiving ISENTRESS 400 mg twice daily and 5% of the control group.

Virologic responses at Week 96 by baseline genotypic and phenotypic sensitivity score are shown in Table 23.

Table 23: Virologic Response at 96 Week Window by Baseline Genotypic/Phenotypic Sensitivity Score
 | Percent with HIV-1 RNA <50 copies/mL At Week 96
 | n | ISENTRESS 400 mg Twice Daily + OBT (N = 462) | n | Placebo + OBT (N = 237)
Phenotypic Sensitivity Score (PSS) [The Phenotypic Sensitivity Score (PSS) and the Genotypic Sensitivity Score (GSS) were defined as the total oral ARTs in OBT to which a subject's viral isolate showed phenotypic sensitivity and genotypic sensitivity, respectively, based upon phenotypic and genotypic resistance tests. Enfuvirtide use in OBT in enfuvirtide-naïve subjects was counted as one active drug in OBT in the GSS and PSS. Similarly, darunavir use in OBT in darunavir-naïve subjects was counted as one active drug in OBT.]
0 | 67 | 43 | 43 | 5
1 | 144 | 58 | 71 | 23
2 | 142 | 61 | 66 | 32
3 or more | 85 | 48 | 48 | 42
Genotypic Sensitivity Score (GSS)
0 | 116 | 39 | 65 | 5
1 | 177 | 62 | 95 | 26
2 | 111 | 61 | 49 | 53
3 or more | 51 | 49 | 23 | 35

Switch of Suppressed Subjects from Lopinavir (+) Ritonavir to Raltegravir

The SWITCHMRK 1 & 2 Phase 3 studies evaluated HIV-1 infected subjects receiving suppressive therapy (HIV-1 RNA <50 copies/mL on a stable regimen of lopinavir 200 mg (+) ritonavir 50 mg 2 tablets twice daily plus at least 2 nucleoside reverse transcriptase inhibitors for >3 months) and randomized them 1:1 to either continue lopinavir (+) ritonavir (n=174 and n=178, SWITCHMRK 1 & 2, respectively) or replace lopinavir (+) ritonavir with ISENTRESS 400 mg twice daily (n=174 and n=176, respectively). The primary virology endpoint was the proportion of subjects with HIV-1 RNA less than 50 copies/mL at Week 24 with a prespecified non-inferiority margin of -12% for each study; and the frequency of adverse events up to 24 weeks.

Subjects with a prior history of virological failure were not excluded and the number of previous antiretroviral therapies was not limited.

These studies were terminated after the primary efficacy analysis at Week 24 because they each failed to demonstrate non-inferiority of switching to ISENTRESS versus continuing on lopinavir (+) ritonavir. In the combined analysis of these studies at Week 24, suppression of HIV-1 RNA to less than 50 copies/mL was maintained in 82.3% of the ISENTRESS group versus 90.3% of the lopinavir (+) ritonavir group. Clinical and laboratory adverse events occurred at similar frequencies in the treatment groups.

14.4 Pediatric Subjects

2 to 18 Years of Age

IMPAACT P1066 is a Phase I/II open-label multicenter trial to evaluate the pharmacokinetic profile, safety, tolerability, and efficacy of raltegravir in HIV infected children. This study enrolled 126 treatment-experienced children and adolescents 2 to 18 years of age. Subjects were stratified by age, enrolling adolescents first and then successively younger children. Subjects were enrolled into cohorts according to age and received the following formulations: Cohort I (12 to less than 18 years old), 400 mg film-coated tablet; Cohort IIa (6 to less than 12 years old), 400 mg film-coated tablet; Cohort IIb (6 to less than 12 years old), chewable tablet; Cohort III (2 to less than 6 years), chewable tablet. Raltegravir was administered with an optimized background regimen.

The initial dose finding stage included intensive pharmacokinetic evaluation. Dose selection was based upon achieving similar raltegravir plasma exposure and trough concentration as seen in adults, and acceptable short term safety. After dose selection, additional subjects were enrolled for evaluation of long term safety, tolerability and efficacy. Of the 126 subjects, 96 received the recommended dose of ISENTRESS [see Dosage and Administration (2.3)].

These 96 subjects had a median age of 13 (range: 2 to 18) years, were 51% female, 34% Caucasian, and 59% Black. At baseline, mean plasma HIV-1 RNA was 4.3 log10 copies/mL, median CD4 cell count was 481 cells/mm^3 (range: 0 – 2361) and median CD4% was 23.3% (range: 0 – 44). Overall, 8% had baseline plasma HIV-1 RNA >100,000 copies/mL and 59% had a CDC HIV clinical classification of category B or C. Most subjects had previously used at least one NNRTI (78%) or one PI (83%).

Ninety-three (97%) subjects 2 to 18 years of age completed 24 weeks of treatment (3 discontinued due to non-compliance). At Week 24, 54% achieved HIV RNA <50 copies/mL; 66% achieved HIV RNA <400 copies/mL. The mean CD4 count (percent) increase from baseline to Week 24 was 119 cells/mm^3 (3.8%).

4 Weeks to Less Than 2 Years of Age

IMPAACT P1066 also enrolled HIV-infected, infants and toddlers 4 weeks to less than 2 years of age (Cohorts IV and V) who had received prior antiretroviral therapy either as prophylaxis for prevention of mother-to-child transmission (PMTCT) and/or as combination antiretroviral therapy for treatment of HIV infection. Raltegravir was administered as an oral suspension without regard to food in combination with an optimized background regimen.

The 26 subjects had a median age of 28 weeks (range: 4 -100), were 35% female, 85% Black and 8% Caucasian. At baseline, mean plasma HIV-1 RNA was 5.7 log10 copies/mL (range: 3.1 – 7), median CD4 cell count was 1400 cells/mm^3 (range: 131 – 3648) and median CD4% was 18.6% (range: 3.3 – 39.3). Overall, 69% had baseline plasma HIV-1 RNA exceeding 100,000 copies/mL and 23% had a CDC HIV clinical classification of category B or C. None of the 26 subjects were completely treatment-naïve. All infants under 6 months of age had received nevirapine or zidovudine for prevention of mother-to-infant transmission, and 43% of subjects greater than 6 months of age had received two or more antiretrovirals.

Of the 26 treated subjects, 23 subjects were included in the Week 24 and 48 efficacy analyses, respectively. All 26 treated subjects were included for safety analyses.

At Week 24, 39% achieved HIV RNA <50 copies/mL and 61% achieved HIV RNA <400 copies/mL. The mean CD4 count (percent) increase from baseline to Week 24 was 500 cells/mm^3 (7.5%).

At Week 48, 44% achieved HIV RNA <50 copies/mL and 61% achieved HIV RNA <400 copies/mL. The mean CD4 count (percent) increase from baseline to Week 48 was 492 cells/mm^3 (7.8%).

16 HOW SUPPLIED/STORAGE AND HANDLING

ISENTRESS tablets 400 mg are pink, oval-shaped, film-coated tablets with "227" on one side. They are supplied as follows:

NDC 0006-0227-61 unit-of-use bottles of 60.

ISENTRESS HD tablets 600 mg are yellow, oval-shaped, film-coated tablets with corporate logo and "242" on one side and plain on the other side. They are supplied as follows:

NDC 0006-3080-01 unit-of-use bottles of 60.

ISENTRESS tablets 100 mg are pale orange, oval-shaped, orange-banana flavored, chewable tablets scored on both sides and imprinted on one face with the corporate logo and "477" on opposite sides of the score. They are supplied as follows:

NDC 0006-0477-61 unit-of-use bottles of 60.

ISENTRESS tablets 25 mg are pale yellow, round, orange-banana flavored, chewable tablets with the corporate logo on one side and "473" on the other side. They are supplied as follows:

NDC 0006-0473-61 unit-of-use bottles of 60.

ISENTRESS for oral suspension 100 mg is a white to off-white granular powder that may contain yellow or beige to tan particles, in child resistant single-use foil packets, packaged as

A kit with two 1 mL syringes, two 3 mL syringes, two 10 mL syringes and two mixing cups. It is supplied as follows:

NDC 0006-3603-61 unit of use carton with 60 packets.
NDC 0006-3603-01 individual packet.

Storage and Handling

400 mg Film-coated Tablets, 600 mg Film-coated Tablets, Chewable Tablets and For Oral Suspension

Store at 20-25°C (68-77°F); excursions permitted to 15-30°C (59-86°F). See USP Controlled Room Temperature.

400 mg Film-coated Tablets, 600 mg Film-coated Tablets and Chewable Tablets

Store in the original package with the bottle tightly closed. Keep the desiccant in the bottle to protect from moisture.

For Oral Suspension

Store in the original container. Do not open foil packet until ready for use.

17 PATIENT COUNSELING INFORMATION

Advise patients to read the FDA-approved patient labeling (Patient Information and Instructions for Use).

Severe and Potentially Life-threatening Rash

Inform patients that severe and potentially life-threatening rash has been reported. Advise patients to immediately contact their healthcare provider if they develop rash. Instruct patients to immediately stop taking ISENTRESS or ISENTRESS HD and other suspect agents, and seek medical attention if they develop a rash associated with any of the following symptoms as it may be a sign of a more serious reaction such as Stevens-Johnson syndrome, toxic epidermal necrolysis or severe hypersensitivity: fever, generally ill feeling, extreme tiredness, muscle or joint aches, blisters, oral lesions, eye inflammation, facial swelling, swelling of the eyes, lips, mouth, breathing difficulty, and/or signs and symptoms of liver problems (e.g., yellowing of the skin or whites of the eyes, dark or tea colored urine, pale colored stools/bowel movements, nausea, vomiting, loss of appetite, or pain, aching or sensitivity on the right side below the ribs). Inform patients that if severe rash occurs, their physician will closely monitor them, order laboratory tests and initiate appropriate therapy.

Immune Reconstitution Syndrome

Advise patients to inform their healthcare provider immediately of any symptoms of infection, as in some patients with advanced HIV infection (AIDS), signs and symptoms of inflammation from previous infections may occur soon after anti-HIV treatment is started [see Warnings and Precautions (5.2)].

Rhabdomyolysis

Before patients begin ISENTRESS or ISENTRESS HD, ask them if they have a history of rhabdomyolysis, myopathy or increased creatine kinase or if they are taking medications known to cause these conditions such as statins, fenofibrate, gemfibrozil or zidovudine [see Adverse Reactions (6.1)].

Instruct patients to immediately report to their healthcare provider any unexplained muscle pain, tenderness, or weakness while taking ISENTRESS.

Phenylketonuria

Alert patients with phenylketonuria that ISENTRESS Chewable Tablets contain phenylalanine [see Warnings and Precautions (5.3)].

Drug Interactions

Inform patients that ISENTRESS or ISENTRESS HD may interact with some drugs and ask them to identify all their current medications including over-the-counter agents [see Drug Interactions (7.2)].

Missed Dosage

Inform patients that it is important to take ISENTRESS or ISENTRESS HD on a regular dosing schedule as instructed by their healthcare provider and to avoid missing doses as it can result in development of resistance [see Dosage and Administration (2)].

Important Administration Instructions

Film-Coated Tablets

Inform patients that the film-coated tablets must be swallowed whole.

Oral Suspension

Instruct parents and/or caregivers to read the Instructions for Use before preparing and administering ISENTRESS for oral suspension to pediatric patients. Instruct parents and/or caregivers that ISENTRESS for oral suspension should be administered within 30 minutes of mixing.

Chewable Tablets

Inform parents and/or caregivers that the chewable tablets can be chewed or swallowed whole. Additionally, the 25 mg chewable tablet may be crushed. Instruct parents and/or caregivers that ISENTRESS 25 mg chewable tablets, if crushed, should be administered immediately [see Dosage and Administration (2.1)].

Pregnancy Registry

Advise patients that there is a pregnancy exposure registry that monitors pregnancy outcomes in women exposed to ISENTRESS or ISENTRESS HD during pregnancy [see Use in Specific Populations (8.1)].

Lactation

Instruct women with HIV-1 infection not to breastfeed because HIV-1 can be passed to the baby in the breast milk [see Use in Specific Populations (8.2)].

Distributed by: Merck Sharp & Dohme LLC
Rahway, NJ 07065, USA

For patent information: www.msd.com/research/patent

Copyright © 2014-2022 Merck & Co., Inc., Rahway, NJ, USA, and its affiliates.
All rights reserved.

uspi-mk0518-mf-2205r038

PATIENT INFORMATION

ISENTRESS® (eye sen tris)
(raltegravir)
film-coated tablets

ISENTRESS® (eye sen tris)
(raltegravir)
chewable tablets

ISENTRESS® HD (eye sen tris HD)
(raltegravir)
film-coated tablets

ISENTRESS® (eye sen tris)
(raltegravir)
for oral suspension

What are ISENTRESS and ISENTRESS HD?

ISENTRESS is a prescription medicine used with other HIV-1 medicines to treat Human Immunodeficiency Virus-1 (HIV-1) infection in adults, and in children weighing at least 4.4 pounds (2 kg). HIV is the virus that causes AIDS (Acquired Immune Deficiency Syndrome).

ISENTRESS HD is a prescription medicine used with other HIV-1 medicines to treat HIV-1 infection in adults, and in children weighing at least 88 pounds (40 kg).
ISENTRESS should not be used in children who weigh less than 4.4 pounds (2 kg).

Before you take ISENTRESS or ISENTRESS HD, tell your doctor about all of your medical conditions, including if you:

- have liver problems
- have a history of a muscle disorder called rhabdomyolysis or myopathy
- have increased levels of creatine kinase in your blood
- have phenylketonuria (PKU). ISENTRESS chewable tablets contain phenylalanine as part of the artificial sweetener, aspartame. The artificial sweetener may be harmful to people with PKU.
- receive kidney dialysis treatment
- are pregnant or plan to become pregnant. It is not known if ISENTRESS or ISENTRESS HD can harm your unborn baby.
  Pregnancy Registry: There is a pregnancy registry for women who take ISENTRESS or ISENTRESS HD during pregnancy. The purpose of this registry is to collect information about the health of you and your baby. Talk to your doctor about how you can take part in this registry.
- are breastfeeding or plan to breastfeed. Do not breastfeed if you take ISENTRESS or ISENTRESS HD.
  - You should not breastfeed if you have HIV-1 because of the risk of passing HIV-1 to your baby.
  - It is not known if ISENTRESS or ISENTRESS HD can pass into your breast milk.
  - Talk with your doctor about the best way to feed your baby.

Tell your doctor about all the medicines you take, including prescription and over-the-counter medicines, vitamins, and herbal supplements. Some medicines interact with ISENTRESS and ISENTRESS HD.

- Keep a list of your medicines to show your doctor and pharmacist.
- You can ask your doctor or pharmacist for a list of medicines that interact with ISENTRESS and ISENTRESS HD.
- Do not start taking a new medicine without telling your doctor. Your doctor can tell you if it is safe to take ISENTRESS or ISENTRESS HD with other medicines.

How should I take ISENTRESS or ISENTRESS HD?

- Take ISENTRESS or ISENTRESS HD exactly as prescribed by your doctor.
- Do not change your dose of ISENTRESS or ISENTRESS HD or stop your treatment without talking with your doctor first.
- Stay under the care of your doctor during treatment with ISENTRESS or ISENTRESS HD.
- ISENTRESS film-coated tablets and ISENTRESS HD film-coated tablets must be swallowed whole.
- ISENTRESS chewable tablets may be chewed or swallowed whole.
  For children who have trouble chewing the 25 mg chewable tablet, the tablet may be crushed and given as follows:
  - Place the tablet(s) in a small, clean cup. For each tablet, add about 1 teaspoonful (5 mL) of liquid (for example, water, juice, or breast milk).
  - Within 2 minutes, the tablet(s) will fall apart in the liquid.
  - Using a spoon, crush any remaining pieces of the tablet(s). Give the child the entire mixture to swallow right away.
  - If any of the dose is left in the cup, add another teaspoonful (5 mL) of liquid, swirl and give to the child right away.
- Do not switch between the film-coated tablet, the chewable tablet, or the oral suspension without talking with your doctor first.
- Do not switch between the ISENTRESS 400 mg film-coated tablet and the ISENTRESS HD 600 mg film-coated tablet if your prescribed dose is 1200 mg.
- Do not run out of ISENTRESS or ISENTRESS HD. The virus in your blood may increase and the virus may become harder to treat. Get a refill of your ISENTRESS or ISENTRESS HD from your doctor or pharmacy before you run out.
- Take ISENTRESS or ISENTRESS HD on a regular dosing schedule as instructed by your doctor. Do not miss doses.
- If you take too much ISENTRESS or ISENTRESS HD, call your doctor or go to the nearest hospital emergency room right away.

If ISENTRESS for oral suspension is prescribed for your child, be sure to read the following information:

- Before giving the first dose of ISENTRESS for oral suspension, read the Instructions for Use booklet that comes with ISENTRESS for oral suspension for information about the correct way to mix and give a dose of ISENTRESS for oral suspension to your child. Keep the booklet and follow it each time you prepare the medicine. Bring this booklet to your child's appointments.
- Make sure your doctor shows you how to mix and give the right dose of ISENTRESS for oral suspension to your child. If you have questions about how to mix or give ISENTRESS for oral suspension, talk with your doctor or pharmacist.
- Give the dose of ISENTRESS for oral suspension within 30 minutes of mixing.
- If your child does not take all of the prescribed dose or spits some of it out, call your doctor to find out what to do.
- Your child's dose will change over time. Make sure you follow your doctor's instructions. Your doctor will tell you if and when to stop giving ISENTRESS to your child.

What are the possible side effects of ISENTRESS or ISENTRESS HD?

ISENTRESS and ISENTRESS HD can cause serious side effects including:

- Severe skin reactions and allergic reactions. Some people who take ISENTRESS or ISENTRESS HD develop severe skin reactions and allergic reactions that can be serious, and may be life-threatening or lead to death.
  - If you develop a rash, call your doctor right away.
  - If you develop a rash with any of the following symptoms, stop using ISENTRESS or ISENTRESS HD and call your doctor or get medical help right away:

- fever
- generally ill feeling
- extreme tiredness
- muscle or joint aches
- blisters or sores in mouth

- blisters or peeling of the skin
- redness or swelling of the eyes
- swelling of the mouth, lips, or face
- problems breathing

Sometimes allergic reactions can affect body organs, such as your liver. Call your doctor right away if you have any of the following signs or symptoms of liver problems:

- yellowing of your skin or whites of your eyes
- dark or tea colored urine
- pale colored stools (bowel movements)

- nausea or vomiting
- loss of appetite
- pain, aching, or tenderness on the right side of your stomach area

- Changes in your immune system (Immune Reconstitution Syndrome) can happen when you start taking HIV-1 medicines. Your immune system may get stronger and begin to fight infections that have been hidden in your body for a long time. Tell your doctor right away if you start having new symptoms after starting your HIV-1 medicine.

The most common side effects of ISENTRESS and ISENTRESS HD include:

- trouble sleeping
- headache

- dizziness
- nausea
- tiredness

Less common side effects of ISENTRESS and ISENTRESS HD include:

- depression
- hepatitis
- genital herpes
- herpes zoster including shingles
- kidney failure

- kidney stones
- indigestion or stomach area pain
- vomiting
- suicidal thoughts and actions
- weakness

Tell your doctor right away if you get unexplained muscle pain, tenderness, or weakness during treatment with ISENTRESS or ISENTRESS HD. These may be signs of a rare serious muscle problem that can lead to kidney problems.

These are not all the possible side effects of ISENTRESS and ISENTRESS HD.

Call your doctor for medical advice about side effects. You may report side effects to FDA at 1-800-FDA-1088.

How should I store ISENTRESS and ISENTRESS HD?

ISENTRESS and ISENTRESS HD film-coated tablets:

- Store ISENTRESS and ISENTRESS HD film-coated tablets at room temperature between 68°F to 77°F (20°C to 25°C).
- Store ISENTRESS and ISENTRESS HD film-coated tablets in the original package with the bottle tightly closed.
- Keep the drying agent (desiccant) in the ISENTRESS and ISENTRESS HD bottle to protect from moisture.

ISENTRESS chewable tablets:

- Store ISENTRESS chewable tablets at room temperature between 68°F to 77°F (20°C to 25°C).
- Store ISENTRESS chewable tablets in the original package with the bottle tightly closed.
- Keep the drying agent (desiccant) in the bottle to protect from moisture.

ISENTRESS for oral suspension:

- Store ISENTRESS for oral suspension at room temperature between 68°F to 77°F (20°C to 25°C).
- Store in the original container. Do not open the foil packet until ready for use.

Keep ISENTRESS and all medicines out of the reach of children.

General information about the safe and effective use of ISENTRESS and ISENTRESS HD

Medicines are sometimes prescribed for purposes other than those listed in a Patient Information Leaflet.

Do not use ISENTRESS or ISENTRESS HD for a condition for which it was not prescribed. Do not give ISENTRESS or ISENTRESS HD to other people, even if they have the same symptoms that you have. It may harm them. You can ask your doctor or pharmacist for information about ISENTRESS or ISENTRESS HD that is written for health professionals.

What are the ingredients in ISENTRESS and ISENTRESS HD?

ISENTRESS 400 mg film-coated tablets:

Active ingredient: raltegravir

Inactive ingredients: calcium phosphate dibasic anhydrous, hypromellose 2208, lactose monohydrate, magnesium stearate, microcrystalline cellulose, poloxamer 407 (contains 0.01% butylated hydroxytoluene as antioxidant), sodium stearyl fumarate.

The film coating contains: black iron oxide, polyethylene glycol 3350, polyvinyl alcohol, red iron oxide, talc and titanium dioxide.

ISENTRESS HD 600 mg film-coated tablets:

Active ingredient: raltegravir

Inactive ingredients: croscarmellose sodium, hypromellose 2910, magnesium stearate, microcrystalline cellulose.

The film coating contains: ferrosoferric oxide, hypromellose 2910, iron oxide yellow, lactose monohydrate, triacetin and titanium dioxide.

The tablet may also contain trace amount of carnauba wax.

ISENTRESS chewable tablets:

Active ingredient: raltegravir

Inactive ingredients: ammonium hydroxide, crospovidone, ethylcellulose 20 cP, fructose, hydroxypropyl cellulose, hypromellose 2910/6cP, magnesium stearate, mannitol, medium chain triglycerides, monoammonium glycyrrhizinate, natural and artificial flavors (orange, banana, and masking that contains aspartame), oleic acid, PEG 400, saccharin sodium, sodium citrate dihydrate, sodium stearyl fumarate, sorbitol, sucralose and yellow iron oxide. The 100 mg chewable tablet also contains red iron oxide.

ISENTRESS for oral suspension:

Active ingredient: raltegravir

Inactive ingredients: ammonium hydroxide, banana with other natural flavors, carboxymethylcellulose sodium, crospovidone, ethylcellulose 20 cP, fructose, hydroxypropyl cellulose, hypromellose 2910/6cP, macrogol/PEG 400, magnesium stearate, maltodextrin, mannitol, medium chain triglycerides, microcrystalline cellulose, monoammonium glycyrrhizinate, oleic acid, sorbitol, sucralose and sucrose.

Distributed by: Merck Sharp & Dohme LLC
Rahway, NJ 07065, USA

For patent information: www.msd.com/research/patent

Copyright © 2007-2022 Merck & Co., Inc., Rahway, NJ, USA, and its affiliates. All rights reserved.

usppi-mk0518-mf-2205r030
For more information go to www.ISENTRESS.com or call 1-800-622-4477.

This Patient Information has been approved by the U.S. Food and Drug Administration.

Revised May 2022

INSTRUCTIONS FOR USE

Bring this booklet to your child's appointments.

ISENTRESS (raltegravir)
for oral suspension

Instructions for Use

for babies and toddlers

Before You Start

Note: Make sure your doctor shows you how to prepare and give ISENTRESS for oral suspension.

- Be sure you understand these instructions before you start. Call your doctor if you have any questions.
- It is very important that you measure the water and ISENTRESS carefully using the correct syringe.
- Before you give ISENTRESS to your child, check the expiration date. The expiration date is printed on the box and the ISENTRESS packets.
- Do not open the ISENTRESS packets until you are ready to mix a dose.
- The amount of ISENTRESS depends on your child's age and weight, so it will change over time.
  Your doctor will tell you the right dose at each check-up after weighing your child.
  Be sure to keep your doctor's appointments so you get new dosing information as your child grows.
  During your child's first week of life, you will give ISENTRESS 1 time a day. After the first week of life, you will give it 2 times a day.
- This booklet tells you how to:
  - Mix ISENTRESS into a liquid form
  - Measure the right dose using a syringe
  - Give mixed ISENTRESS to your child
  - Clean up

Kit Contents

- Prescription (on box)

- 2 mixing cups

- Instructions for Use (this booklet)
- Prescribing Information
- 6 syringes

- 60 packets of ISENTRESS

2 blue (10mL) syringes

2 green (3mL) syringes

2 white (1mL) syringes

The kit has an extra cup and set of syringes in case one is lost or damaged.

Do not use any damaged cups or syringes.

Step 1. Get ready

- Put your child in a safe place. You will need both hands to prepare ISENTRESS.
- Wash your hands with soap and water.
- Take out what you need from the kit as shown below to make 1 dose and place on a clean surface:

1 mixing cup
(Using the tab on the mixing cup, pull open the lid)

1 packet of ISENTRESS

a clean glass

3 syringes
(Have one of each size ready, but you will only need 1 or 2, depending on the prescribed dose)

Step 2. Fill a clean glass with water

Fill a clean glass with room-temperature drinking water from your sink or use bottled water.

Step 3. Fill the blue syringe with water

Push the plunger of the blue syringe into the syringe as far as it goes.

Put the tip of the syringe into the glass of water. Pull back the plunger to draw up water into the syringe. Stop when you get to the 10mL mark.

Step 4. Check for air bubbles

Hold the syringe with tip up. Tap it with your finger to move any air bubbles up towards the tip.
Slowly push up on the plunger to make the air come out. You may see some drops of water come out.

Re-check the amount of water in the syringe. If it is less than 10mL, put the tip back into the water and pull back on the plunger until you get to the 10mL mark.

Step 5. Add the 10mL of water to the mixing cup

Add the 10 mL of water from the syringe to the mixing cup by pushing all the way down on the plunger.

Step 6. Add ISENTRESS to the mixing cup

Note before adding ISENTRESS:
Make sure you and your child are ready! After mixing ISENTRESS, use it within 30 minutes. Throw away any leftover ISENTRESS after you have given the dose to your child.

Take 1 packet of ISENTRESS and shake the powder to the bottom of the packet.

Tear or cut open the packet at the dotted line and add all of the powder to the water in the mixing cup. Make sure the packet is completely empty.

Step 7. Mix ISENTRESS and water

Snap the lid of the mixing cup shut.
Gently swirl the mixing cup for 45 seconds in a circular motion to mix the powder and water. Use a clock or timer to time for 45 seconds. Do not shake the mixture.

Check to make sure the powder is mixed. If it is not mixed, swirl it some more. The mixture should look cloudy.

Step 8. Check your prescription

Find the dose amount in 'mL' prescribed by your doctor. This is written on the prescription label on the box from your pharmacy.

Remember that the dose may change each time you go to the doctor, so make sure you check the prescribed dose each time. Be sure to go to all of your doctor's appointments so your child gets the right dose!

Step 9. Choose the syringe you need

Your doctor will prescribe the dose in milliliters (mL). Choose the right syringe for your child's dose:

WHITE
(1mL) for 1mL
or less

GREEN
(3mL)
for 1.5mL
to 3mL

BLUE
(10mL)
for 3.5mL
to 10mL

Then find the mL mark on the syringe that matches your child's dose.

Step 10. Measure ISENTRESS

Push the plunger into the barrel of the syringe as far as it goes.

Put the tip of the syringe into the cup of the mixed ISENTRESS and pull back on the plunger.
Stop when you get to the line that matches your child's prescribed dose.

IMPORTANT:

- Your child's dose may be different from the one shown in this figure.
- There will usually be some leftover mixed ISENTRESS in the mixing cup.

Step 11. Check for air bubbles

Hold the syringe with tip up. Tap it with your finger to move any air bubbles up towards the tip.
Slowly push the plunger to make the air come out. You may see some drops of medicine come out.

Re-check the amount of ISENTRESS in the syringe. If it is less than the prescribed dose, put the tip back into the cup of mixed ISENTRESS and pull back on the plunger until you get to the right dose mark.

Step 12. Give ISENTRESS to your child

Place the tip of the syringe inside your child's mouth so that it touches either the right or left cheek.

Slowly push in the plunger to give the dose of mixed ISENTRESS to your child. If your child fusses, take the tip of the syringe out of the mouth and try again. It is important that your child takes all of the prescribed dose (a little left in the syringe tip is OK).

IMPORTANT:
If your child does not take all of the prescribed dose or spits some of it out, call your doctor to find out what to do.

Step 13. Clean up

Pour the leftover mixed ISENTRESS into the trash.
Do not pour it into the sink.

Pull the plungers out of any syringes you used.

Hand wash the syringes, plungers, and mixing cup with warm water and dish soap. Do not wash in the dishwasher.

Rinse with water and let air dry.
Put everything in a clean, dry place.

How should I store ISENTRESS?

Store the ISENTRESS for oral suspension kit at room temperature between 68°F to 77°F (20°C to 25°C).

Store in the original container.

Keep ISENTRESS and all medicines out of the reach of children.

Be sure to keep your doctor's appointments so you always know how much ISENTRESS to give to your child.

For more information, go to www.ISENTRESS.com or call 1-800-622-4477.

Distributed by: Merck Sharp & Dohme LLC
Rahway, NJ 07065, USA

For patent information: www.msd.com/research/patent

Copyright © 2013-2022 Merck & Co., Inc., Rahway, NJ, USA, and its affiliates.
All rights reserved.

ifu-mk0518-mf-2205r002
Revised May/2022

PRINCIPAL DISPLAY PANEL - 400 mg Tablet Bottle Label

NDC 0006-0227-61

Isentress®
(raltegravir) tablets

400 mg

Each tablet contains 434.4 mg raltegravir
potassium, equivalent to 400 mg raltegravir.

USUAL DOSAGE: See Package Insert.

Rx only

60 Tablets

PRINCIPAL DISPLAY PANEL - 600 mg Bottle Label

NDC 0006-3080-01

Isentress® HD
(raltegravir) tablets

600 mg

RECOMMENDED DOSAGE: Two tablets once daily.

See Package Insert.

Each tablet contains 651.6 mg raltegravir
potassium, equivalent to
600 mg raltegravir.

Rx only

60 Tablets

PRINCIPAL DISPLAY PANEL - 100 mg Tablet Bottle Label

NDC 0006-0477-61

Isentress®
(raltegravir) CHEWABLE Tablets

100 mg

For Pediatric Use

Phenylketonurics: contains phenylalanine (a component
of aspartame) 0.10 mg per 100 mg chewable tablet.

Rx only

60 Tablets

PRINCIPAL DISPLAY PANEL - 25 mg Tablet Bottle Label

NDC 0006-0473-61

Isentress®
(raltegravir) CHEWABLE Tablets

25 mg

For Pediatric Use

Phenylketonurics: contains phenylalanine (a component
of aspartame) 0.05 mg per 25 mg chewable tablet.

Rx only

60 Tablets

PACKAGE LABEL

PRINCIPAL DISPLAY PANEL - 100 mg Packet Carton

NDC 0006-3603-61

Isentress®
(raltegravir)
For Oral Suspension

100 mg

For Pediatric Use

For Oral Administration Only

Each packet contains 108.6 mg raltegravir potassium, equivalent to 100 mg raltegravir.

Rx only

60 packets

Multi-Dose Kit
DIRECTIONS FOR USE:
See instructions for use
booklet and package insert
for additional information.